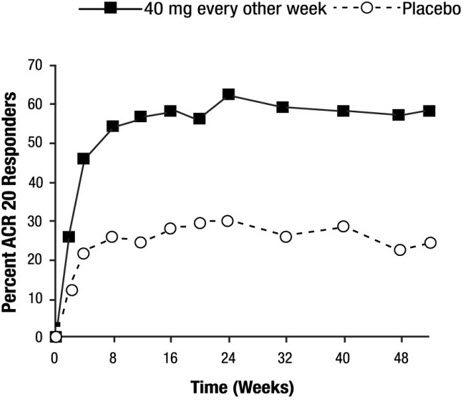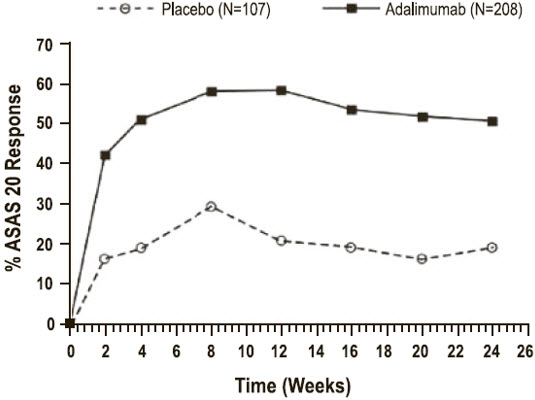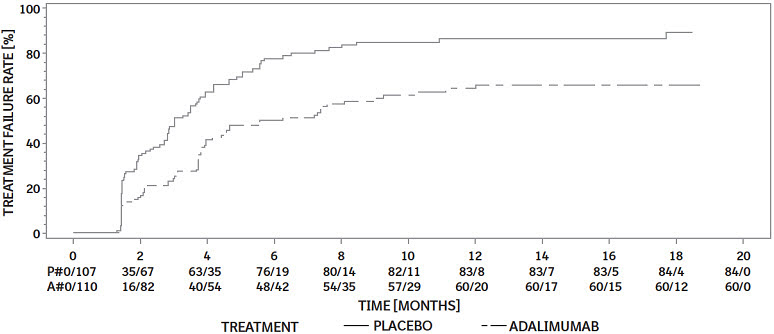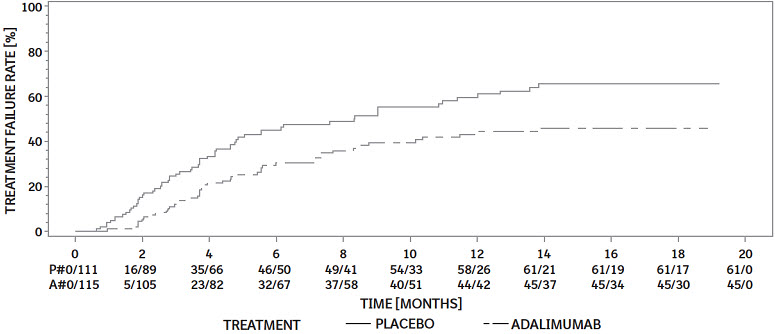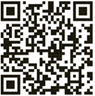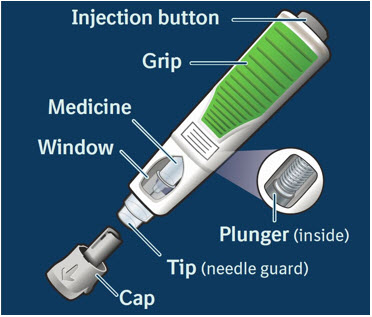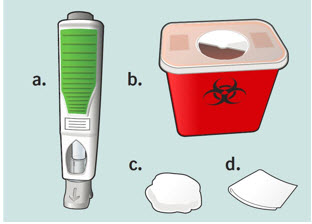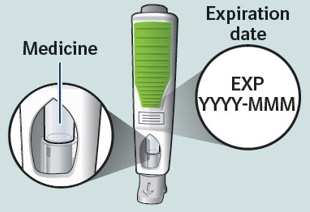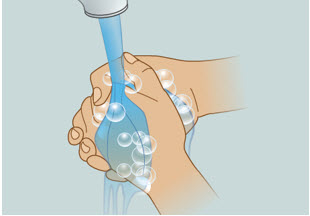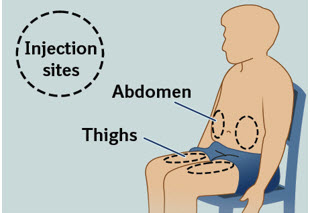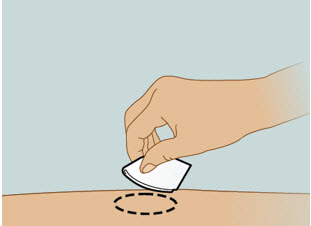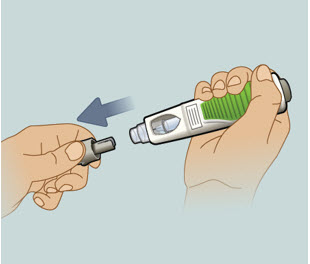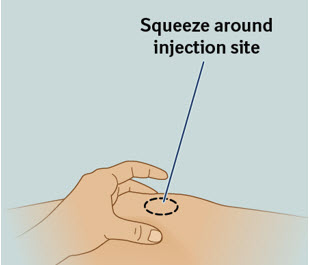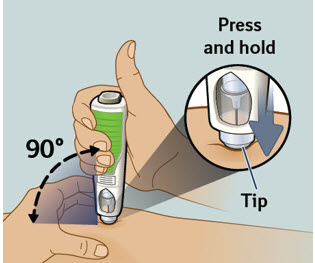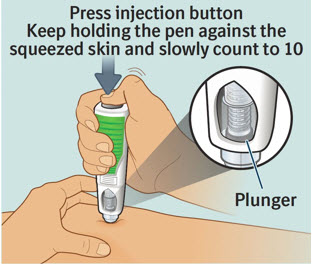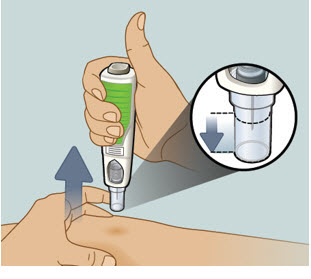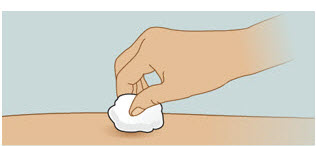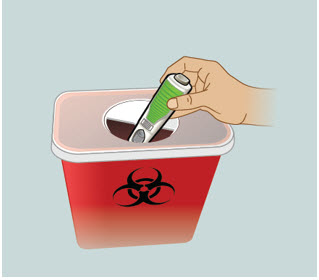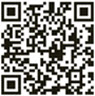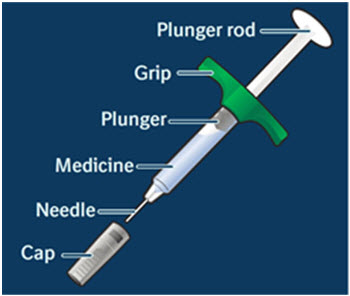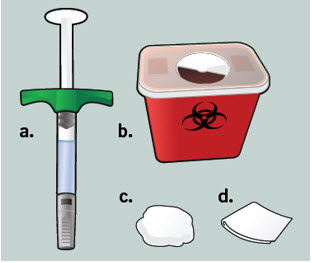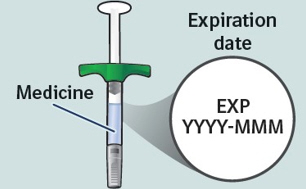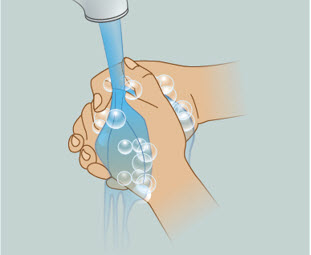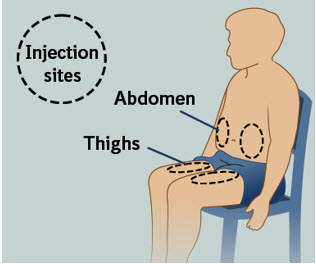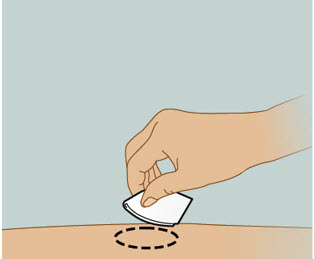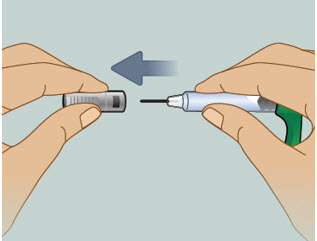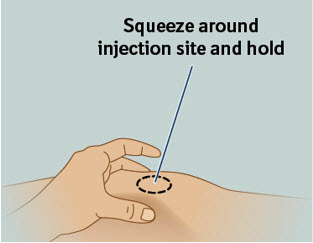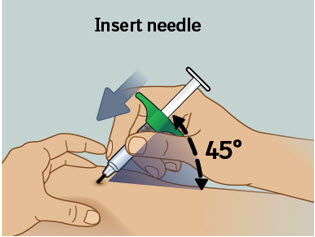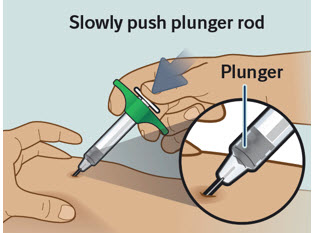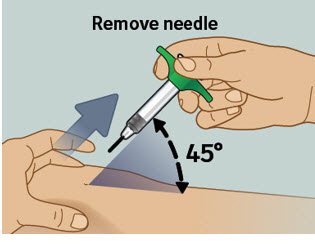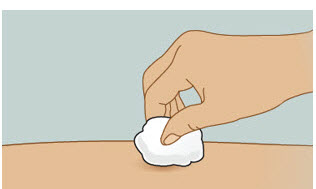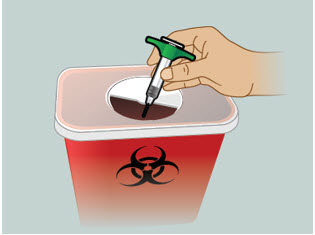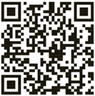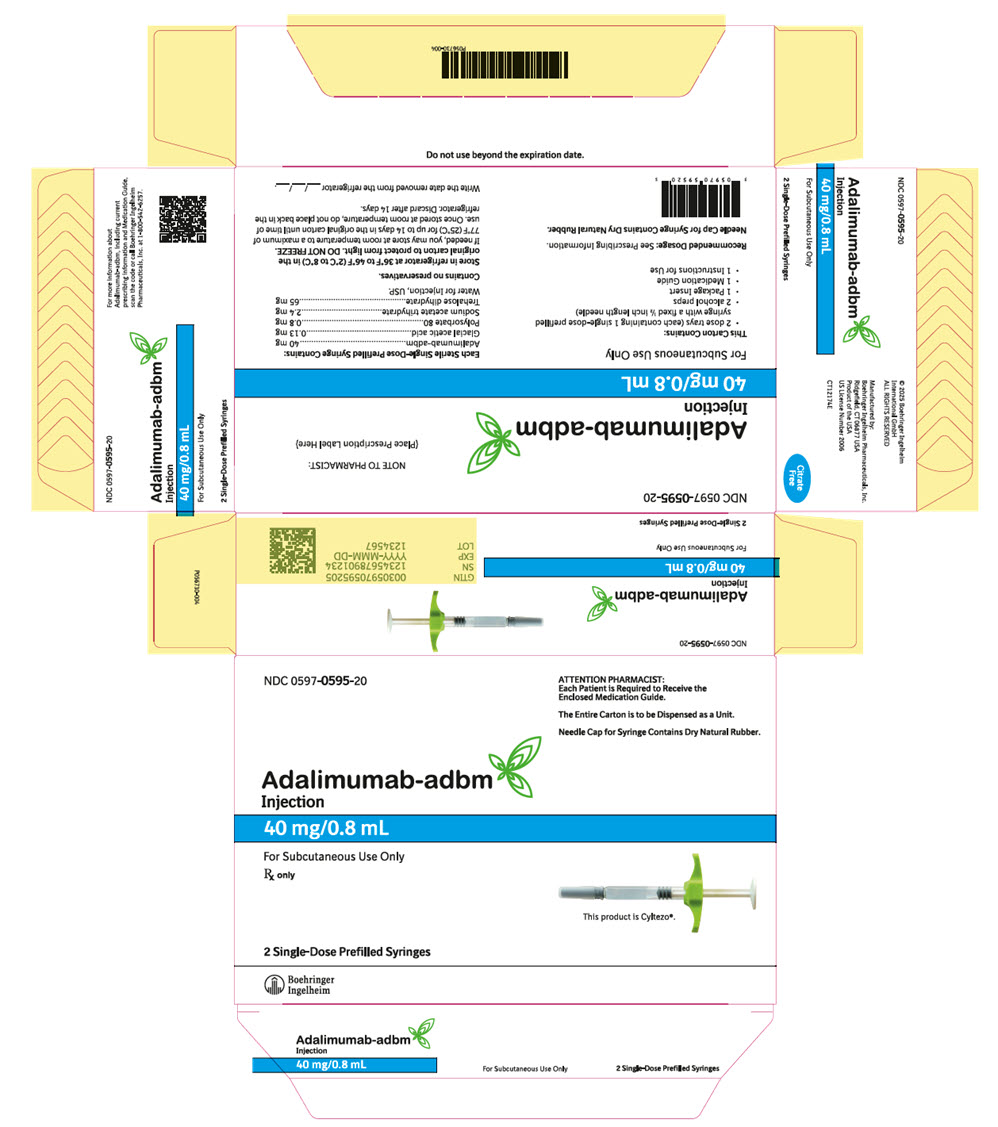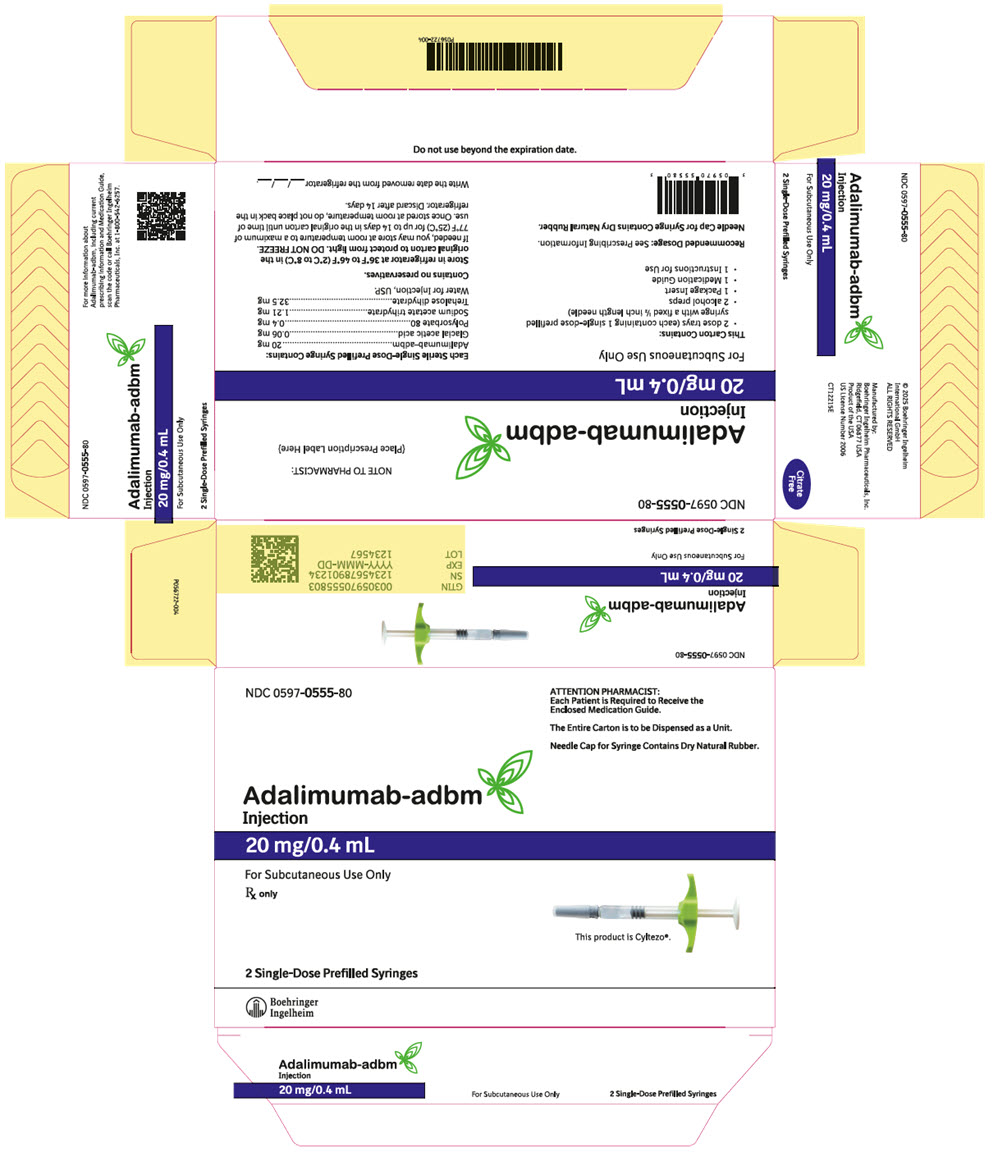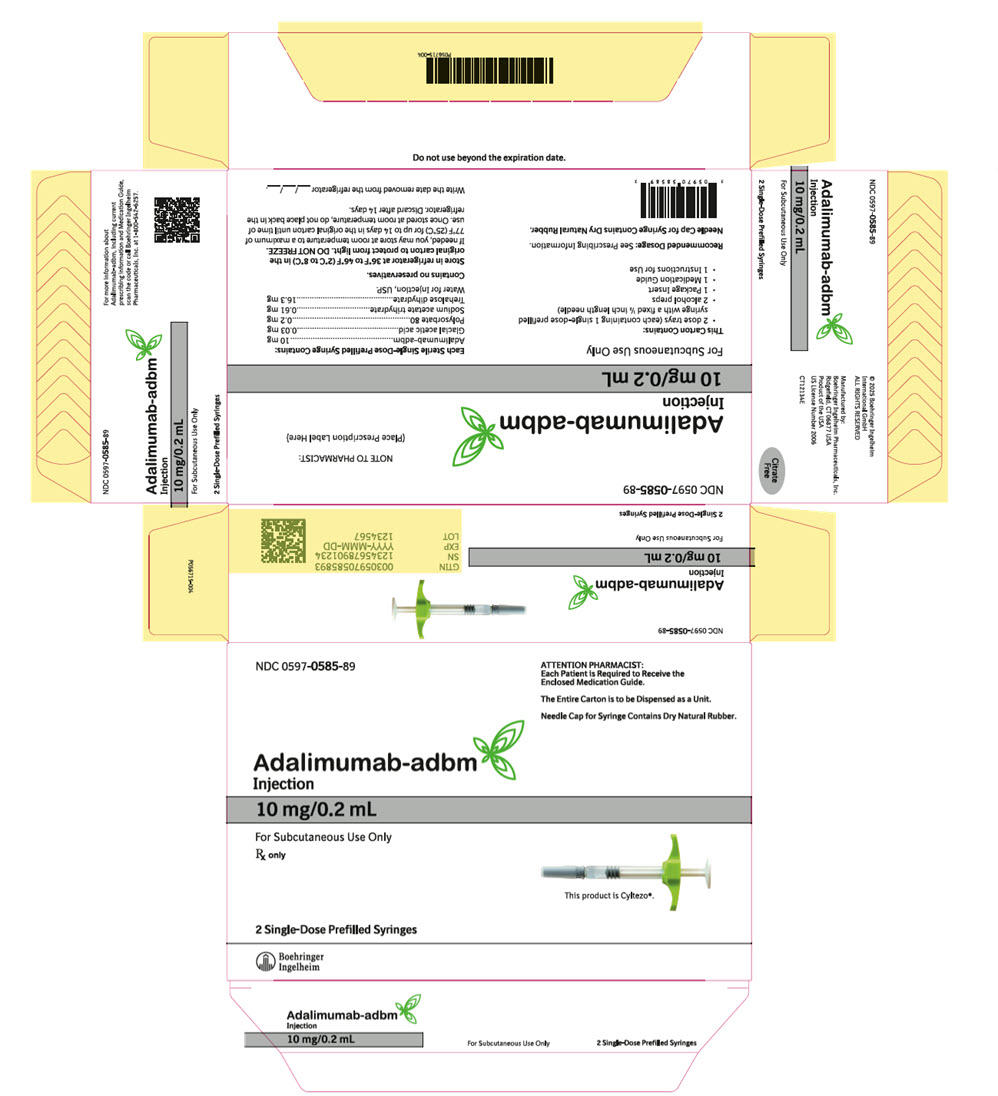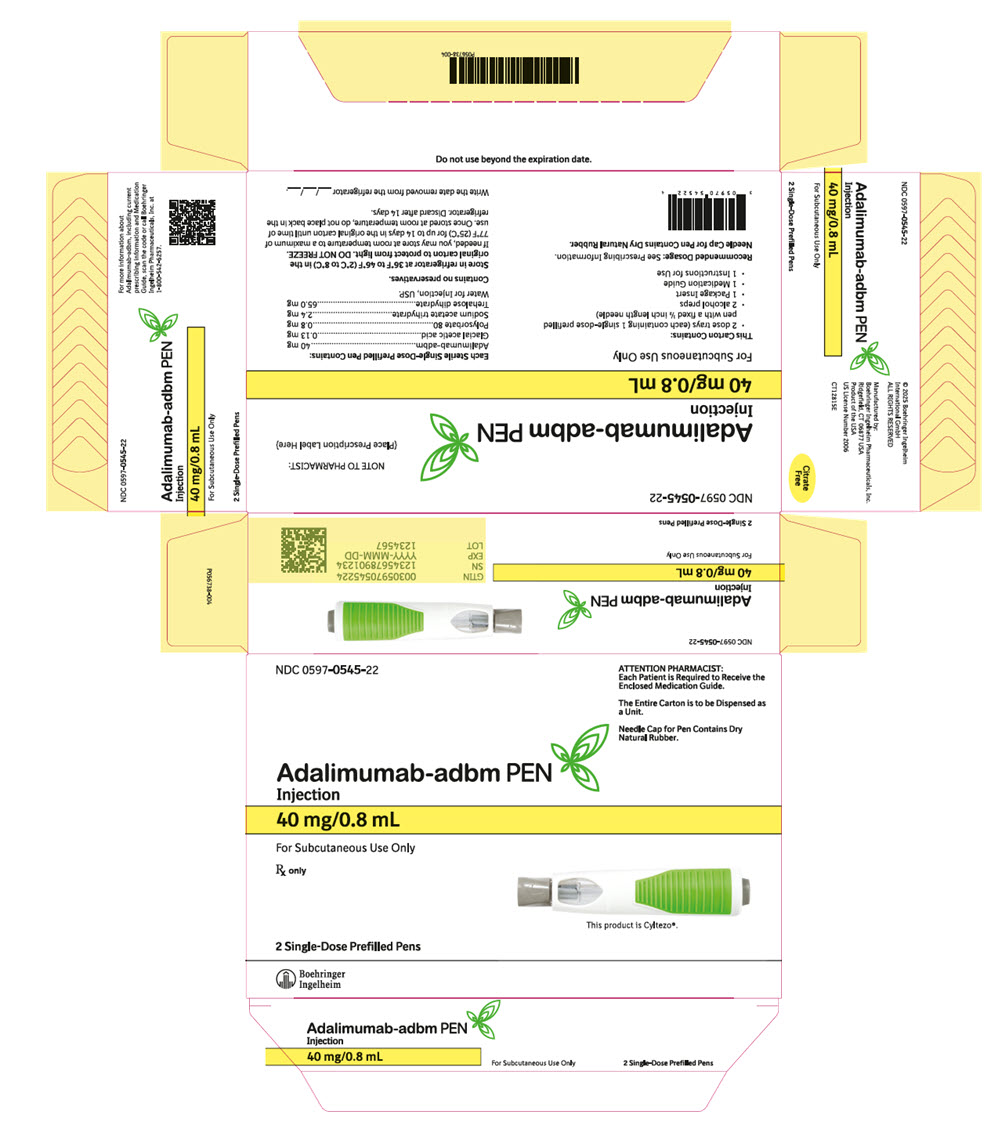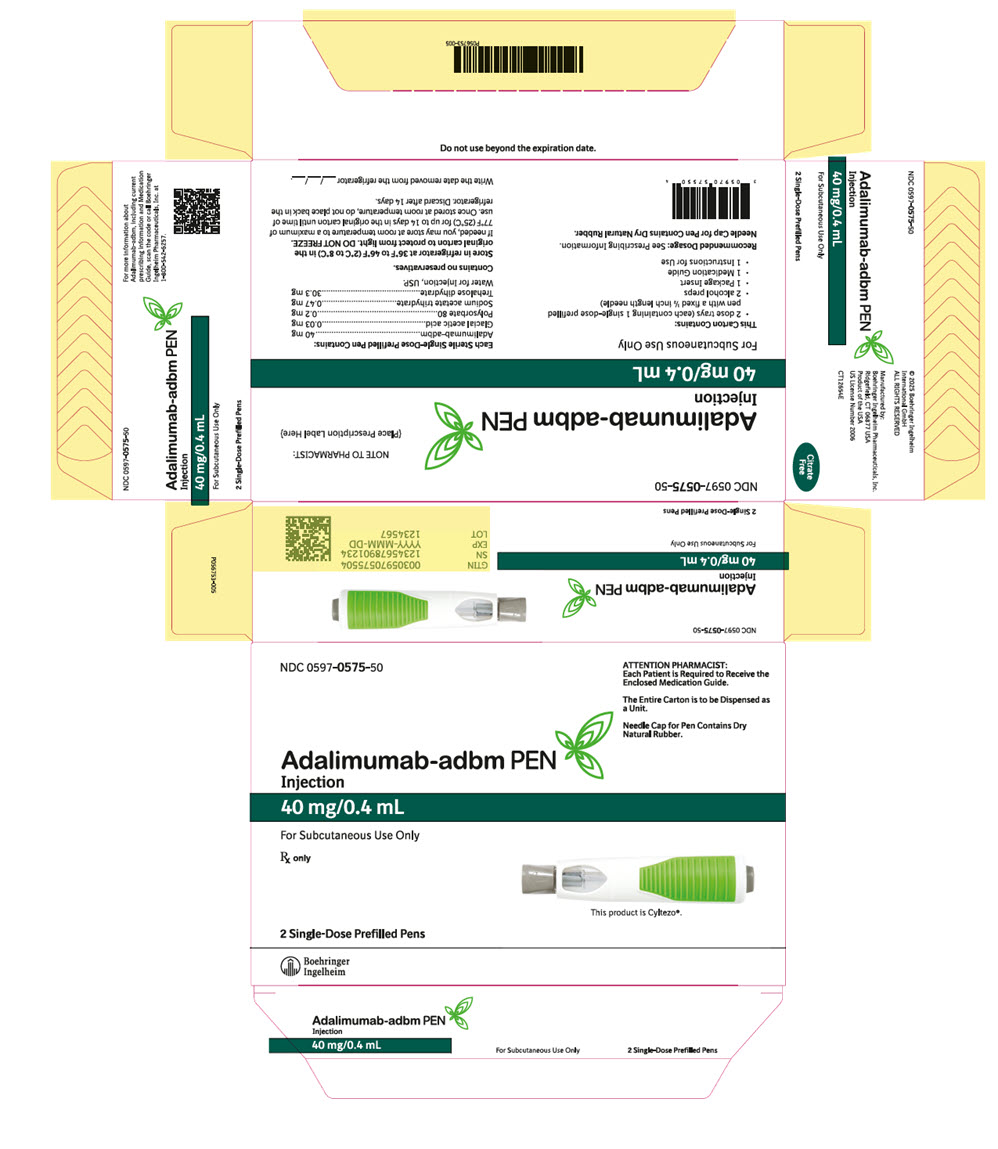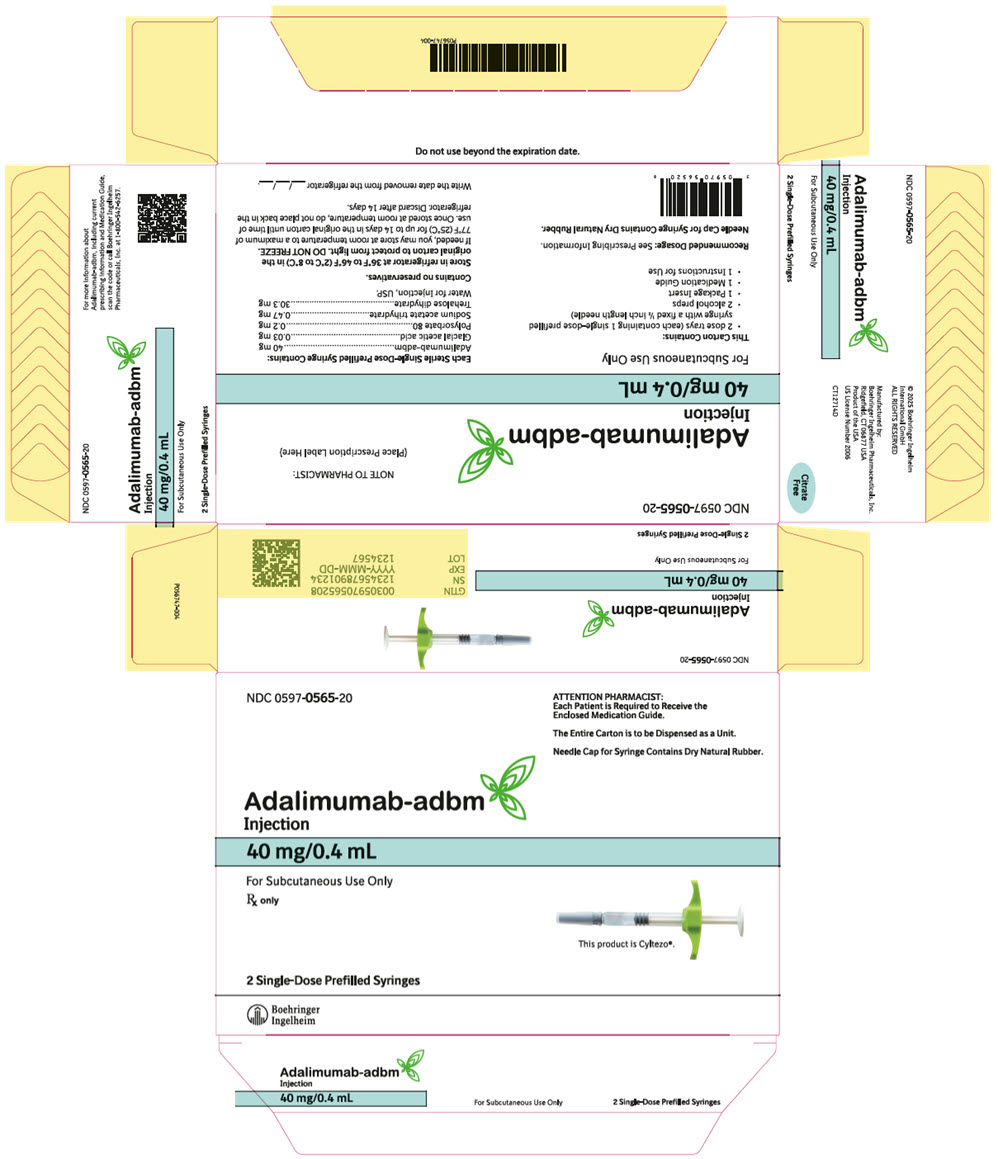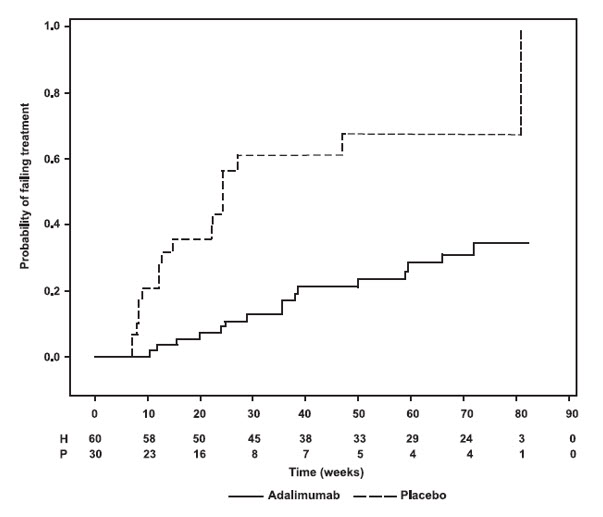 DRUG LABEL: Adalimumab-adbm
NDC: 0597-0595 | Form: KIT | Route: SUBCUTANEOUS
Manufacturer: Boehringer Ingelheim Pharmaceuticals, Inc.
Category: prescription | Type: HUMAN PRESCRIPTION DRUG LABEL
Date: 20251112

ACTIVE INGREDIENTS: ADALIMUMAB 40 mg/0.8 mL; ISOPROPYL ALCOHOL 0.7 mL/1 mL
INACTIVE INGREDIENTS: WATER

HIGHLIGHTS OF PRESCRIBING INFORMATION

These highlights do not include all the information needed to use ADALIMUMAB-ADBM safely and effectively. See full prescribing information for ADALIMUMAB-ADBM.
ADALIMUMAB-ADBM injection, for subcutaneous use
Initial U.S. Approval: 2017
This product is CYLTEZO® (adalimumab-adbm). CYLTEZO (adalimumab-adbm) is biosimilar [Biosimilar means that the biological product is approved based on data demonstrating that it is highly similar to an FDA-approved biological product, known as a reference product, and that there are no clinically meaningful differences between the biosimilar product and the reference product. Biosimilarity of Adalimumab-adbm has been demonstrated for the condition(s) of use (e.g., indication(s), dosing regimen(s)), strength(s), dosage form(s), and route(s) of administration described in its Full Prescribing Information.] to HUMIRA® (adalimumab).

WARNING: SERIOUS INFECTIONS AND MALIGNANCY

See full prescribing information for complete boxed warning.

SERIOUS INFECTIONS (5.1, 6.1):

- Increased risk of serious infections leading to hospitalization or death, including tuberculosis (TB), bacterial sepsis, invasive fungal infections (such as histoplasmosis), and infections due to other opportunistic pathogens.
- Discontinue Adalimumab-adbm if a patient develops a serious infection or sepsis during treatment.
- Perform test for latent TB; if positive, start treatment for TB prior to starting Adalimumab-adbm.
- Monitor all patients for active TB during treatment, even if initial latent TB test is negative.

MALIGNANCY (5.2):

- Lymphoma and other malignancies, some fatal, have been reported in children and adolescent patients treated with TNF blockers including adalimumab products.
- Post-marketing cases of hepatosplenic T-cell lymphoma (HSTCL), a rare type of T-cell lymphoma, have occurred in adolescent and young adults with inflammatory bowel disease treated with TNF blockers including adalimumab products.

RECENT MAJOR CHANGES

Indications and Usage,
Hidradenitis Suppurativa (1.8) | 10/2025
Uveitis (1.9) | 10/2025
Dosage and Administration,
Juvenile Idiopathic Arthritis or Pediatric Uveitis (2.3) | 10/2025
Hidradenitis Suppurativa (2.7) | 10/2025
Warnings and Precautions, Autoimmunity (5.9) | 10/2025

1 INDICATIONS AND USAGE

Adalimumab-adbm is a tumor necrosis factor (TNF) blocker indicated for:

- Reducing signs and symptoms, inducing major clinical response, inhibiting the progression of structural damage, and improving physical function in adult patients with moderately to severely active rheumatoid arthritis. (1.1)
- Reducing signs and symptoms of moderately to severely active polyarticular juvenile idiopathic arthritis in patients 2 years of age and older. (1.2)
- Reducing signs and symptoms, inhibiting the progression of structural damage, and improving physical function in adult patients with active psoriatic arthritis. (1.3)
- Reducing signs and symptoms in adult patients with active ankylosing spondylitis. (1.4)
- Treatment of moderately to severely active Crohn's disease in adults and pediatric patients 6 years of age and older. (1.5)
- Treatment of moderately to severely active ulcerative colitis in adult patients. (1.6)
  Limitations of Use: Effectiveness has not been established in patients who have lost response to or were intolerant to TNF blockers.
- Treatment of adult patients with moderate to severe chronic plaque psoriasis who are candidates for systemic therapy or phototherapy, and when other systemic therapies are medically less appropriate. (1.7)
- Treatment of moderate to severe hidradenitis suppurativa in patients 12 years of age and older. (1.8)
- Treatment of non-infectious intermediate, posterior, and panuveitis in adults and pediatric patients 2 years of age and older. (1.9)

2 DOSAGE AND ADMINISTRATION

- Administer by subcutaneous injection (2)

Rheumatoid Arthritis, Psoriatic Arthritis, Ankylosing Spondylitis (2.2):

- Adults: 40 mg every other week.

Some patients with RA not receiving methotrexate may benefit from increasing the dosage to 40 mg every week or 80 mg every other week.

Juvenile Idiopathic Arthritis or Pediatric Uveitis (2.3):

Pediatric Weight 2 Years of Age and Older | Recommended Dosage
10 kg (22 lbs) to less than 15 kg (33 lbs) | 10 mg every other week
15 kg (33 lbs) to less than 30 kg (66 lbs) | 20 mg every other week
30 kg (66 lbs) and greater | 40 mg every other week

Crohn's Disease (2.4):

- Adults: 160 mg on Day 1 (given in one day or split over two consecutive days); 80 mg on Day 15; and 40 mg every other week starting on Day 29.
- Pediatric Patients 6 Years of Age and Older:

Pediatric Weight | Recommended Dosage
Pediatric Weight | Days 1 and 15 | Starting on Day 29
17 kg (37 lbs) to less than 40 kg (88 lbs) | Day 1: 80 mg Day 15: 40 mg | 20 mg every other week
40 kg (88 lbs) and greater | Day 1: 160 mg (single dose or split over two consecutive days) Day 15: 80 mg | 40 mg every other week

Ulcerative Colitis (2.5):

- Adults: 160 mg on Day 1 (given in one day or split over two consecutive days), 80 mg on Day 15 and 40 mg every other week starting on Day 29. Discontinue in patients without evidence of clinical remission by eight weeks (Day 57).

Plaque Psoriasis or Adult Uveitis (2.6):

- Adults: 80 mg initial dose, followed by 40 mg every other week starting one week after initial dose.

Hidradenitis Suppurativa (2.7):

- Adults:
  - Day 1: 160 mg (given in one day or split over two consecutive days)
  - Day 15: 80 mg
  - Day 29 and subsequent doses: 40 mg every week or 80 mg every other week
- Adolescents 12 years of age and older:

Adolescent Weight | Recommended Dosage
30 kg (66 lbs) to less than 60 kg (132 lbs) | Day 1: 80 mg Day 8 and subsequent doses: 40 mg every other week
60 kg (132 lbs) and greater | Day 1: 160 mg (given in one day or split over two consecutive days) Day 15: 80 mg Day 29 and subsequent doses: 40 mg every week or 80 mg every other week

3 DOSAGE FORMS AND STRENGTHS

Injection:

- Single-dose prefilled pen (Adalimumab-adbm Pen): 40 mg/0.8 mL, 40 mg/0.4 mL (3)
- Single-dose prefilled glass syringe: 40 mg/0.8 mL, 40 mg/0.4 mL, 20 mg/0.4 mL, 10 mg/0.2 mL (3)

4 CONTRAINDICATIONS

None (4)

5 WARNINGS AND PRECAUTIONS

- Serious infections: Do not start Adalimumab-adbm during an active infection. If an infection develops, monitor carefully, and stop Adalimumab-adbm if infection becomes serious. (5.1)
- Invasive fungal infections: For patients who develop a systemic illness on Adalimumab-adbm, consider empiric antifungal therapy for those who reside or travel to regions where mycoses are endemic. (5.1)
- Malignancies: Incidence of malignancies was greater in adalimumab-treated patients than in controls (5.2)
- Anaphylaxis or serious hypersensitivity reactions may occur (5.3)
- Hepatitis B virus reactivation: Monitor HBV carriers during and several months after therapy. If reactivation occurs, stop Adalimumab-adbm and begin anti-viral therapy. (5.4)
- Demyelinating disease: Exacerbation or new onset, may occur. (5.5)
- Cytopenias, pancytopenia: Advise patients to seek immediate medical attention if symptoms develop, and consider stopping Adalimumab-adbm. (5.6)
- Heart failure: Worsening or new onset, may occur. (5.8)
- Autoimmunity: Stop Adalimumab-adbm if lupus-like syndrome or autoimmune hepatitis develop. (5.9)

6 ADVERSE REACTIONS

Most common adverse reactions (>10%) are: infections (e.g., upper respiratory, sinusitis), injection site reactions, headache and rash. (6.1)

To report SUSPECTED ADVERSE REACTIONS, contact Boehringer Ingelheim Pharmaceuticals, Inc. at (800) 542-6257 or FDA at 1-800-FDA-1088 or www.fda.gov/medwatch.

7 DRUG INTERACTIONS

- Abatacept: Increased risk of serious infection. (5.1, 5.11, 7.2)
- Anakinra: Increased risk of serious infection. (5.1, 5.7, 7.2)
- Live vaccines: Avoid use with Adalimumab-adbm. (5.10, 7.3)

FULL PRESCRIBING INFORMATION

WARNING: SERIOUS INFECTIONS AND MALIGNANCY

SERIOUS INFECTIONS

Patients treated with adalimumab products, including Adalimumab-adbm, are at increased risk for developing serious infections that may lead to hospitalization or death [see Warnings and Precautions (5.1)]. Most patients who developed these infections were taking concomitant immunosuppressants such as methotrexate or corticosteroids.

Discontinue Adalimumab-adbm if a patient develops a serious infection or sepsis.

Reported infections include:

- Active tuberculosis (TB), including reactivation of latent TB. Patients with TB have frequently presented with disseminated or extrapulmonary disease. Test patients for latent TB before Adalimumab-adbm use and during therapy. Initiate treatment for latent TB prior to Adalimumab-adbm use.
- Invasive fungal infections, including histoplasmosis, coccidioidomycosis, candidiasis, aspergillosis, blastomycosis, and pneumocystosis. Patients with histoplasmosis or other invasive fungal infections may present with disseminated, rather than localized, disease. Antigen and antibody testing for histoplasmosis may be negative in some patients with active infection. Consider empiric anti-fungal therapy in patients at risk for invasive fungal infections who develop severe systemic illness.
- Bacterial, viral and other infections due to opportunistic pathogens, including Legionella and Listeria.

Carefully consider the risks and benefits of treatment with Adalimumab-adbm prior to initiating therapy in patients with chronic or recurrent infection.

Monitor patients closely for the development of signs and symptoms of infection during and after treatment with Adalimumab-adbm, including the possible development of TB in patients who tested negative for latent TB infection prior to initiating therapy [see Warnings and Precautions (5.1) and Adverse Reactions (6.1)].

MALIGNANCY

Lymphoma and other malignancies, some fatal, have been reported in children and adolescent patients treated with TNF blockers including adalimumab products [see Warnings and Precautions (5.2)]. Post-marketing cases of hepatosplenic T-cell lymphoma (HSTCL), a rare type of T-cell lymphoma, have been reported in patients treated with TNF blockers including adalimumab products. These cases have had a very aggressive disease course and have been fatal. The majority of reported TNF blocker cases have occurred in patients with Crohn's disease or ulcerative colitis and the majority were in adolescent and young adult males. Almost all these patients had received treatment with azathioprine or 6-mercaptopurine (6-MP) concomitantly with a TNF blocker at or prior to diagnosis. It is uncertain whether the occurrence of HSTCL is related to use of a TNF blocker or a TNF blocker in combination with these other immunosuppressants [see Warnings and Precautions (5.2)].

1 INDICATIONS AND USAGE

1.1 Rheumatoid Arthritis

Adalimumab-adbm is indicated for reducing signs and symptoms, inducing major clinical response, inhibiting the progression of structural damage, and improving physical function in adult patients with moderately to severely active rheumatoid arthritis. Adalimumab-adbm can be used alone or in combination with methotrexate or other non-biologic disease-modifying anti-rheumatic drugs (DMARDs).

1.2 Juvenile Idiopathic Arthritis

Adalimumab-adbm is indicated for reducing signs and symptoms of moderately to severely active polyarticular juvenile idiopathic arthritis in patients 2 years of age and older. Adalimumab-adbm can be used alone or in combination with methotrexate.

1.3 Psoriatic Arthritis

Adalimumab-adbm is indicated for reducing signs and symptoms, inhibiting the progression of structural damage, and improving physical function in adult patients with active psoriatic arthritis. Adalimumab-adbm can be used alone or in combination with non-biologic DMARDs.

1.4 Ankylosing Spondylitis

Adalimumab-adbm is indicated for reducing signs and symptoms in adult patients with active ankylosing spondylitis.

1.5 Crohn's Disease

Adalimumab-adbm is indicated for the treatment of moderately to severely active Crohn's disease in adults and pediatric patients 6 years of age and older.

1.6 Ulcerative Colitis

Adalimumab-adbm is indicated for the treatment of moderately to severely active ulcerative colitis in adult patients.

Limitations of Use

The effectiveness of adalimumab products has not been established in patients who have lost response to or were intolerant to TNF blockers [see Clinical Studies (14.7)].

1.7 Plaque Psoriasis

Adalimumab-adbm is indicated for the treatment of adult patients with moderate to severe chronic plaque psoriasis who are candidates for systemic therapy or phototherapy, and when other systemic therapies are medically less appropriate. Adalimumab-adbm should only be administered to patients who will be closely monitored and have regular follow-up visits with a physician [see Warnings and Precautions (5)].

1.8 Hidradenitis Suppurativa

Adalimumab-adbm is indicated for the treatment of moderate to severe hidradenitis suppurativa in patients 12 years of age and older.

1.9 Uveitis

Adalimumab-adbm is indicated for the treatment of non-infectious intermediate, posterior, and panuveitis in adults and pediatric patients 2 years of age and older.

2 DOSAGE AND ADMINISTRATION

2.1 Recommended Tuberculosis Evaluation

Prior to initiating Adalimumab-adbm and periodically during therapy, evaluate patients for active tuberculosis and test for latent infection [see Warnings and Precautions (5.1)].

2.2 Recommended Dosage in Rheumatoid Arthritis, Psoriatic Arthritis, and Ankylosing Spondylitis

The recommended subcutaneous dosage of Adalimumab-adbm for adult patients with rheumatoid arthritis (RA), psoriatic arthritis (PsA), or ankylosing spondylitis (AS) [see Indications and Usage (1.1, 1.3, 1.4)] is 40 mg administered every other week. Methotrexate (MTX), other non-biologic DMARDs, glucocorticoids, nonsteroidal anti-inflammatory drugs (NSAIDs), and/or analgesics may be continued during treatment with Adalimumab-adbm. In the treatment of RA, some patients not taking concomitant MTX may derive additional benefit from increasing the dosage of Adalimumab-adbm to 40 mg every week or 80 mg every other week.

2.3 Recommended Dosage in Juvenile Idiopathic Arthritis or Pediatric Patients with Uveitis

The recommended subcutaneous dosage of Adalimumab-adbm for pediatric patients 2 years of age and older with polyarticular juvenile idiopathic arthritis (JIA) or pediatric uveitis [see Indications and Usage (1.2, 1.9)], based on weight, is shown below. MTX, glucocorticoids, NSAIDs, and/or analgesics may be continued during treatment with Adalimumab-adbm.

Pediatric Weight (2 Years of Age and older) | Recommended Dosage
10 kg (22 lbs) to less than 15 kg (33 lbs) | 10 mg every other week
15 kg (33 lbs) to less than 30 kg (66 lbs) | 20 mg every other week
30 kg (66 lbs) and greater | 40 mg every other week

Adalimumab products have not been studied in patients with polyarticular JIA or pediatric uveitis less than 2 years of age or in patients with a weight below 10 kg.

2.4 Recommended Dosage in Crohn's Disease

Subcutaneous Adult Dosage Regimen

The recommended subcutaneous dosage of Adalimumab-adbm for adult patients with moderately to severely active Crohn's disease (CD) is 160 mg initially on Day 1 (given in one day or split over two consecutive days), followed by 80 mg two weeks later (Day 15). Two weeks later (Day 29) begin a dosage of 40 mg every other week. Aminosalicylates and/or corticosteroids may be continued during treatment with Adalimumab-adbm. Azathioprine, 6-mercaptopurine (6-MP) [see Warnings and Precautions (5.2)] or MTX may be continued during treatment with Adalimumab-adbm if necessary.

Subcutaneous Pediatric Dosage Regimen

The recommended subcutaneous dosage of Adalimumab-adbm for pediatric patients 6 years of age and older with moderately to severely active Crohn's disease (CD), based on body weight, is shown below:

Pediatric Weight | Recommended Dosage
Pediatric Weight | Days 1 through 15 | Starting on Day 29
17 kg (37 lbs) to less than 40 kg (88 lbs) | Day 1: 80 mg Day 15: 40 mg | 20 mg every other week
40 kg (88 lbs) and greater | Day 1: 160 mg (single dose or split over two consecutive days) Day 15: 80 mg | 40 mg every other week

2.5 Recommended Dosage in Ulcerative Colitis

Subcutaneous Adult Dosage Regimen

The recommended subcutaneous dosage of Adalimumab-adbm for adult patients with moderately to severely active ulcerative colitis is 160 mg initially on Day 1 (given in one day or split over two consecutive days), followed by 80 mg two weeks later (Day 15). Two weeks later (Day 29) continue with a dosage of 40 mg every other week.

Discontinue Adalimumab-adbm in adult patients without evidence of clinical remission by eight weeks (Day 57) of therapy. Aminosalicylates and/or corticosteroids may be continued during treatment with Adalimumab-adbm. Azathioprine and 6-mercaptopurine (6-MP) [see Warnings and Precautions (5.2)] may be continued during treatment with Adalimumab-adbm if necessary.

2.6 Recommended Dosage in Plaque Psoriasis or Adults with Uveitis

The recommended subcutaneous dosage of Adalimumab-adbm for adult patients with plaque psoriasis (Ps) or uveitis (UV) [see Indications and Usage (1.7, 1.9)] is an initial dose of 80 mg, followed by 40 mg given every other week starting one week after the initial dose. The use of adalimumab products in moderate to severe chronic Ps beyond one year has not been evaluated in controlled clinical studies.

2.7 Recommended Dosage in Hidradenitis Suppurativa

Subcutaneous Adult Dosage Regimen

The recommended subcutaneous dosage of Adalimumab-adbm for adult patients with moderate to severe hidradenitis suppurativa (HS) is an initial dose of 160 mg (given in one day or split over two consecutive days), followed by 80 mg two weeks later (Day 15). Begin 40 mg weekly or 80 mg every other week dosing two weeks later (Day 29).

Subcutaneous Pediatric Dosage Regimen

The recommended subcutaneous dosage of Adalimumab-adbm for pediatric patients 12 years of age and older weighing at least 30 kg with moderate to severe hidradenitis suppurativa (HS), based on body weight, is shown below [see Use in Specific Populations (8.4) and Clinical Pharmacology (12.3)]:

Body Weight of Pediatric Patients (12 years of age and older) | Recommended Dosage
30 kg (66 lbs) to less than 60 kg (132 lbs) | - Day 1: 80 mg - Day 8 and subsequent doses: 40 mg every other week
60 kg (132 lbs) and greater | - Day 1: 160 mg (given in one day or split over two consecutive days); - Day 15: 80 mg - Day 29 and subsequent doses: 40 mg every week or 80 mg every other week

2.8 General Considerations for Administration

Adalimumab-adbm is intended for use under the guidance and supervision of a physician. A patient may self-inject Adalimumab-adbm or a caregiver may inject Adalimumab-adbm using either the Adalimumab-adbm Pen or prefilled syringe if a physician determines that it is appropriate, and with medical follow-up, as necessary, after proper training in subcutaneous injection technique.

Adalimumab-adbm can be taken out of the refrigerator for 15 to 30 minutes before injecting to allow the liquid to come to room temperature. Do not remove the cap while allowing it to reach room temperature. Carefully inspect the solution in the Adalimumab-adbm Pen or prefilled syringe for particulate matter and discoloration prior to subcutaneous administration. If particulates and discolorations are noted, do not use the product. Adalimumab-adbm does not contain preservatives; therefore, discard unused portions of drug remaining from the syringe. NOTE: Instruct patients sensitive to latex not to handle the needle cap of the Adalimumab-adbm 40 mg/0.8 mL and 40 mg/0.4 mL Pen or 40 mg/0.8 mL, 40 mg/0.4 mL, 20 mg/0.4 mL, and 10 mg/0.2 mL prefilled syringe because they contain natural rubber latex [see How Supplied/Storage and Handling (16)].

Instruct patients using the Adalimumab-adbm Pen or prefilled syringe to inject the full amount in the syringe, according to the directions provided in the Instructions for Use [see Instructions for Use].

Injections should occur at separate sites in the thigh or abdomen. Rotate injection sites and do not give injections into areas where the skin is tender, bruised, red or hard.

If a dose is missed, administer the dose as soon as possible. Thereafter, resume dosing at the regular scheduled time.

3 DOSAGE FORMS AND STRENGTHS

Adalimumab-adbm is a clear to slightly opalescent and colorless to slightly yellow solution available as:

Pen (Adalimumab-adbm Pen)

- Injection: 40 mg/0.8 mL in a single-dose pen.
- Injection: 40 mg/0.4 mL in a single-dose pen.

Prefilled Syringe

- Injection: 40 mg/0.8 mL in a single-dose, 1 mL prefilled glass syringe.
- Injection: 40 mg/0.4 mL in a single-dose, 1 mL prefilled glass syringe.
- Injection: 20 mg/0.4 mL in a single-dose, 1 mL prefilled glass syringe.
- Injection: 10 mg/0.2 mL in a single-dose, 1 mL prefilled glass syringe.

4 CONTRAINDICATIONS

None.

5 WARNINGS AND PRECAUTIONS

5.1 Serious Infections

Patients treated with adalimumab products, including Adalimumab-adbm, are at increased risk for developing serious infections involving various organ systems and sites that may lead to hospitalization or death. Opportunistic infections due to bacterial, mycobacterial, invasive fungal, viral, parasitic, or other opportunistic pathogens including aspergillosis, blastomycosis, candidiasis, coccidioidomycosis, histoplasmosis, legionellosis, listeriosis, pneumocystosis and tuberculosis have been reported with TNF blockers. Patients have frequently presented with disseminated rather than localized disease.

The concomitant use of a TNF blocker and abatacept or anakinra was associated with a higher risk of serious infections in patients with rheumatoid arthritis (RA); therefore, the concomitant use of Adalimumab-adbm and these biologic products is not recommended in the treatment of patients with RA [see Warnings and Precautions (5.7, 5.11) and Drug Interactions (7.2)].

Treatment with Adalimumab-adbm should not be initiated in patients with an active infection, including localized infections. Patients 65 years of age and older, patients with co-morbid conditions and/or patients taking concomitant immunosuppressants (such as corticosteroids or methotrexate), may be at greater risk of infection. Consider the risks and benefits of treatment prior to initiating therapy in patients:

- with chronic or recurrent infection;
- who have been exposed to tuberculosis;
- with a history of an opportunistic infection;
- who have resided or traveled in areas of endemic tuberculosis or endemic mycoses, such as histoplasmosis, coccidioidomycosis, or blastomycosis; or
- with underlying conditions that may predispose them to infection.

Tuberculosis

Cases of reactivation of tuberculosis and new onset tuberculosis infections have been reported in patients receiving adalimumab products, including patients who have previously received treatment for latent or active tuberculosis. Reports included cases of pulmonary and extrapulmonary (i.e., disseminated) tuberculosis. Evaluate patients for tuberculosis risk factors and test for latent infection prior to initiating Adalimumab-adbm and periodically during therapy.

Treatment of latent tuberculosis infection prior to therapy with TNF blocking agents has been shown to reduce the risk of tuberculosis reactivation during therapy. Prior to initiating Adalimumab-adbm, assess if treatment for latent tuberculosis is needed; and consider an induration of ≥5 mm a positive tuberculin skin test result, even for patients previously vaccinated with Bacille Calmette-Guerin (BCG).

Consider anti-tuberculosis therapy prior to initiation of Adalimumab-adbm in patients with a past history of latent or active tuberculosis in whom an adequate course of treatment cannot be confirmed, and for patients with a negative test for latent tuberculosis but having risk factors for tuberculosis infection. Despite prophylactic treatment for tuberculosis, cases of reactivated tuberculosis have occurred in patients treated with adalimumab products. Consultation with a physician with expertise in the treatment of tuberculosis is recommended to aid in the decision whether initiating anti-tuberculosis therapy is appropriate for an individual patient.

Strongly consider tuberculosis in the differential diagnosis in patients who develop a new infection during Adalimumab-adbm treatment, especially in patients who have previously or recently traveled to countries with a high prevalence of tuberculosis, or who have had close contact with a person with active tuberculosis.

Monitoring

Closely monitor patients for the development of signs and symptoms of infection during and after treatment with Adalimumab-adbm, including the development of tuberculosis in patients who tested negative for latent tuberculosis infection prior to initiating therapy. Tests for latent tuberculosis infection may also be falsely negative while on therapy with Adalimumab-adbm.

Discontinue Adalimumab-adbm if a patient develops a serious infection or sepsis. For a patient who develops a new infection during treatment with Adalimumab-adbm, closely monitor them, perform a prompt and complete diagnostic workup appropriate for an immunocompromised patient, and initiate appropriate antimicrobial therapy.

Invasive Fungal Infections

If patients develop a serious systemic illness and they reside or travel in regions where mycoses are endemic, consider invasive fungal infection in the differential diagnosis. Antigen and antibody testing for histoplasmosis may be negative in some patients with active infection. Consider appropriate empiric antifungal therapy, taking into account both the risk for severe fungal infection and the risks of antifungal therapy, while a diagnostic workup is being performed. To aid in the management of such patients, consider consultation with a physician with expertise in the diagnosis and treatment of invasive fungal infections.

5.2 Malignancies

Consider the risks and benefits of TNF-blocker treatment including Adalimumab-adbm prior to initiating therapy in patients with a known malignancy other than a successfully treated non-melanoma skin cancer (NMSC) or when considering continuing a TNF blocker in patients who develop a malignancy.

Malignancies in Adults

In the controlled portions of clinical trials of some TNF-blockers, including adalimumab products, more cases of malignancies have been observed among TNF-blocker-treated adult subjects compared to control-treated adult subjects. During the controlled portions of 39 global adalimumab clinical trials in adult patients with rheumatoid arthritis (RA), psoriatic arthritis (PsA), ankylosing spondylitis (AS), Crohn's disease (CD), ulcerative colitis (UC), plaque psoriasis (Ps), hidradenitis suppurativa (HS) and uveitis (UV), malignancies, other than non-melanoma (basal cell and squamous cell) skin cancer, were observed at a rate (95% confidence interval) of 0.7 (0.48, 1.03) per 100 patient-years among 7973 adalimumab-treated subjects versus a rate of 0.7 (0.41, 1.17) per 100 patient-years among 4848 control-treated subjects (median duration of treatment of 4 months for adalimumab-treated subjects and 4 months for control-treated subjects). In 52 global controlled and uncontrolled clinical trials of adalimumab in adult patients with RA, PsA, AS, CD, UC, Ps, HS and UV, the most frequently observed malignancies, other than lymphoma and NMSC, were breast, colon, prostate, lung, and melanoma. The malignancies in adalimumab-treated subjects in the controlled and uncontrolled portions of the studies were similar in type and number to what would be expected in the general U.S. population according to the SEER database (adjusted for age, gender, and race).^1

In controlled trials of other TNF blockers in adult patients at higher risk for malignancies (i.e., subjects with COPD with a significant smoking history and cyclophosphamide-treated patients with Wegener's granulomatosis), a greater portion of malignancies occurred in the TNF blocker group compared to the control group.

Non-Melanoma Skin Cancer

During the controlled portions of 39 global adalimumab clinical trials in adult patients with RA, PsA, AS, CD, UC, Ps, HS and UV, the rate (95% confidence interval) of NMSC was 0.8 (0.52, 1.09) per 100 patient-years among adalimumab-treated subjects and 0.2 (0.10, 0.59) per 100 patient-years among control-treated subjects. Examine all patients, and in particular patients with a medical history of prior prolonged immunosuppressant therapy or psoriasis patients with a history of PUVA treatment for the presence of NMSC prior to and during treatment with Adalimumab-adbm.

Lymphoma and Leukemia

In the controlled portions of clinical trials of all the TNF-blockers in adults, more cases of lymphoma have been observed among TNF-blocker-treated subjects compared to control-treated subjects. In the controlled portions of 39 global adalimumab clinical trials in adult patients with RA, PsA, AS, CD, UC, Ps, HS and UV, 2 lymphomas occurred among 7973 adalimumab-treated subjects versus 1 among 4848 control-treated subjects. In 52 global controlled and uncontrolled clinical trials of adalimumab in adult patients with RA, PsA, AS, CD, UC, Ps, HS and UV with a median duration of approximately 0.7 years, including 24,605 subjects and over 40,215 patient-years of adalimumab, the observed rate of lymphomas was approximately 0.11 per 100 patient-years. This is approximately 3-fold higher than expected in the general U.S. population according to the SEER database (adjusted for age, gender, and race).^1 Rates of lymphoma in clinical trials of adalimumab cannot be compared to rates of lymphoma in clinical trials of other TNF blockers and may not predict the rates observed in a broader patient population. Patients with RA and other chronic inflammatory diseases, particularly those with highly active disease and/or chronic exposure to immunosuppressant therapies, may be at a higher risk (up to several fold) than the general population for the development of lymphoma, even in the absence of TNF blockers. Post-marketing cases of acute and chronic leukemia have been reported in association with TNF-blocker use in RA and other indications. Even in the absence of TNF-blocker therapy, patients with RA may be at a higher risk (approximately 2-fold) than the general population for the development of leukemia.

Malignancies in Pediatric Patients and Young Adults

Malignancies, some fatal, have been reported among children, adolescents, and young adults who received treatment with TNF-blockers (initiation of therapy ≤18 years of age), of which Adalimumab-adbm is a member. Approximately half the cases were lymphomas, including Hodgkin's and non-Hodgkin's lymphoma. The other cases represented a variety of different malignancies and included rare malignancies usually associated with immunosuppression and malignancies that are not usually observed in children and adolescents. The malignancies occurred after a median of 30 months of therapy (range 1 to 84 months). Most of the patients were receiving concomitant immunosuppressants. These cases were reported post-marketing and are derived from a variety of sources including registries and spontaneous postmarketing reports.

Postmarketing cases of hepatosplenic T-cell lymphoma (HSTCL), a rare type of T-cell lymphoma, have been reported in patients treated with TNF blockers including adalimumab products. These cases have had a very aggressive disease course and have been fatal. The majority of reported TNF blocker cases have occurred in patients with Crohn's disease or ulcerative colitis and the majority were in adolescent and young adult males. Almost all of these patients had received treatment with the immunosuppressants azathioprine or 6-mercaptopurine (6-MP) concomitantly with a TNF blocker at or prior to diagnosis. It is uncertain whether the occurrence of HSTCL is related to use of a TNF blocker or a TNF blocker in combination with these other immunosuppressants. The potential risk with the combination of azathioprine or 6-mercaptopurine and Adalimumab-adbm should be carefully considered.

5.3 Hypersensitivity Reactions

Anaphylaxis and angioneurotic edema have been reported following administration of adalimumab products. If an anaphylactic or other serious allergic reaction occurs, immediately discontinue administration of Adalimumab-adbm and institute appropriate therapy. In clinical trials of adalimumab, hypersensitivity reactions (e.g., rash, anaphylactoid reaction, fixed drug reaction, non-specified drug reaction, urticaria) have been observed.

5.4 Hepatitis B Virus Reactivation

Use of TNF blockers, including Adalimumab-adbm, may increase the risk of reactivation of hepatitis B virus (HBV) in patients who are chronic carriers of this virus. In some instances, HBV reactivation occurring in conjunction with TNF blocker therapy has been fatal. The majority of these reports have occurred in patients concomitantly receiving other medications that suppress the immune system, which may also contribute to HBV reactivation. Evaluate patients at risk for HBV infection for prior evidence of HBV infection before initiating TNF blocker therapy. Exercise caution in prescribing TNF blockers for patients identified as carriers of HBV. Adequate data are not available on the safety or efficacy of treating patients who are carriers of HBV with anti-viral therapy in conjunction with TNF blocker therapy to prevent HBV reactivation. For patients who are carriers of HBV and require treatment with TNF blockers, closely monitor such patients for clinical and laboratory signs of active HBV infection throughout therapy and for several months following termination of therapy. In patients who develop HBV reactivation, stop Adalimumab-adbm and initiate effective anti-viral therapy with appropriate supportive treatment. The safety of resuming TNF blocker therapy after HBV reactivation is controlled is not known. Therefore, exercise caution when considering resumption of Adalimumab-adbm therapy in this situation and monitor patients closely.

5.5 Neurologic Reactions

Use of TNF blocking agents, including adalimumab products, has been associated with rare cases of new onset or exacerbation of clinical symptoms and/or radiographic evidence of central nervous system demyelinating disease, including multiple sclerosis (MS) and optic neuritis, and peripheral demyelinating disease, including Guillain-Barré syndrome. Exercise caution in considering the use of Adalimumab-adbm in patients with preexisting or recent-onset central or peripheral nervous system demyelinating disorders; discontinuation of Adalimumab-adbm should be considered if any of these disorders develop. There is a known association between intermediate uveitis and central demyelinating disorders.

5.6 Hematological Reactions

Rare reports of pancytopenia including aplastic anemia have been reported with TNF blocking agents. Adverse reactions of the hematologic system, including medically significant cytopenia (e.g., thrombocytopenia, leukopenia) have been infrequently reported with adalimumab products. The causal relationship of these reports to adalimumab products remains unclear. Advise all patients to seek immediate medical attention if they develop signs and symptoms suggestive of blood dyscrasias or infection (e.g., persistent fever, bruising, bleeding, pallor) while on Adalimumab-adbm. Consider discontinuation of Adalimumab-adbm therapy in patients with confirmed significant hematologic abnormalities.

5.7 Increased Risk of Infection When Used with Anakinra

Concurrent use of anakinra (an interleukin-1 antagonist) and another TNF-blocker, was associated with a greater proportion of serious infections and neutropenia and no added benefit compared with the TNF-blocker alone in patients with RA. Therefore, the combination of Adalimumab-adbm and anakinra is not recommended [see Drug Interactions (7.2)].

5.8 Heart Failure

Cases of worsening congestive heart failure (CHF) and new onset CHF have been reported with TNF blockers. Cases of worsening CHF have also been observed with adalimumab products. Adalimumab products have not been formally studied in patients with CHF; however, in clinical trials of another TNF blocker, a higher rate of serious CHF-related adverse reactions was observed. Exercise caution when using Adalimumab-adbm in patients who have heart failure and monitor them carefully.

5.9 Autoimmunity

Treatment with adalimumab products may result in the formation of autoantibodies and, rarely, in the development of a lupus-like syndrome or autoimmune hepatitis [see Adverse Reactions (6.1, 6.3)]. If a patient develops symptoms and findings suggestive of a lupus-like syndrome or autoimmune hepatitis following treatment with Adalimumab-adbm, discontinue treatment and evaluate the patient.

5.10 Immunizations

In a placebo-controlled clinical trial of patients with RA, no difference was detected in anti-pneumococcal antibody response between adalimumab and placebo treatment groups when the pneumococcal polysaccharide vaccine and influenza vaccine were administered concurrently with adalimumab. Similar proportions of subjects developed protective levels of anti-influenza antibodies between adalimumab and placebo treatment groups; however, titers in aggregate to influenza antigens were moderately lower in patients receiving adalimumab. The clinical significance of this is unknown. Patients on Adalimumab-adbm may receive concurrent vaccinations, except for live vaccines. No data are available on the secondary transmission of infection by live vaccines in patients receiving adalimumab products.

It is recommended that pediatric patients, if possible, be brought up to date with all immunizations in agreement with current immunization guidelines prior to initiating Adalimumab-adbm therapy. Patients on Adalimumab-adbm may receive concurrent vaccinations, except for live vaccines.

The safety of administering live or live-attenuated vaccines in infants exposed to adalimumab products in utero is unknown. Risks and benefits should be considered prior to vaccinating (live or live-attenuated) exposed infants [see Use in Specific Populations (8.1, 8.4)].

5.11 Increased Risk of Infection When Used with Abatacept

In controlled trials, the concurrent administration of TNF-blockers and abatacept was associated with a greater proportion of serious infections than the use of a TNF-blocker alone; the combination therapy, compared to the use of a TNF-blocker alone, has not demonstrated improved clinical benefit in the treatment of RA. Therefore, the combination of abatacept with TNF-blockers including Adalimumab-adbm is not recommended [see Drug Interactions (7.2)].

6 ADVERSE REACTIONS

The following clinically significant adverse reactions are described elsewhere in the labeling:

- Serious Infections [see Warnings and Precautions (5.1)]
- Malignancies [see Warnings and Precautions (5.2)]
- Hypersensitivity Reactions [see Warnings and Precautions (5.3)]
- Hepatitis B Virus Reactivation [see Warnings and Precautions (5.4)]
- Neurologic Reactions [see Warnings and Precautions (5.5)]
- Hematological Reactions [see Warnings and Precautions (5.6)]
- Heart Failure [see Warnings and Precautions (5.8)]
- Autoimmunity [see Warnings and Precautions (5.9)]

6.1 Clinical Trials Experience

Because clinical trials are conducted under widely varying conditions, adverse reaction rates observed in the clinical trials of a drug cannot be directly compared to rates in the clinical trials of another drug and may not reflect the rates observed in practice.

The most common adverse reaction with adalimumab was injection site reactions. In placebo-controlled trials, 20% of subjects treated with adalimumab developed injection site reactions (erythema and/or itching, hemorrhage, pain or swelling), compared to 14% of subjects receiving placebo. Most injection site reactions were described as mild and generally did not necessitate drug discontinuation.

The proportion of subjects who discontinued treatment due to adverse reactions during the double-blind, placebo-controlled portion of studies in subjects with RA (i.e., Studies RA-I, RA-II, RA-III and RA-IV) was 7% for subjects taking adalimumab and 4% for placebo-treated subjects. The most common adverse reactions leading to discontinuation of adalimumab in these RA studies were clinical flare reaction (0.7%), rash (0.3%) and pneumonia (0.3%).

Infections

In the controlled portions of the 39 global adalimumab clinical trials in adult subjects with RA, PsA, AS, CD, UC, Ps, HS and UV, the rate of serious infections was 4.3 per 100 patient-years in 7973 adalimumab-treated subjects versus a rate of 2.9 per 100 patient-years in 4848 control-treated subjects. Serious infections observed included pneumonia, septic arthritis, prosthetic and post-surgical infections, erysipelas, cellulitis, diverticulitis, and pyelonephritis [see Warnings and Precautions (5.1)].

Tuberculosis and Opportunistic Infections

In 52 global controlled and uncontrolled clinical trials in RA, PsA, AS, CD, UC, Ps, HS and UV that included 24,605 adalimumab-treated subjects, the rate of reported active tuberculosis was 0.20 per 100 patient-years and the rate of positive PPD conversion was 0.09 per 100 patient-years. In a subgroup of 10,113 U.S. and Canadian adalimumab-treated subjects, the rate of reported active TB was 0.05 per 100 patient-years and the rate of positive PPD conversion was 0.07 per 100 patient-years. These trials included reports of miliary, lymphatic, peritoneal, and pulmonary TB. Most of the TB cases occurred within the first eight months after initiation of therapy and may reflect recrudescence of latent disease. In these global clinical trials, cases of serious opportunistic infections have been reported at an overall rate of 0.05 per 100 patient-years. Some cases of serious opportunistic infections and TB have been fatal [see Warnings and Precautions (5.1)].

Autoantibodies

In the rheumatoid arthritis controlled trials, 12% of subjects treated with adalimumab and 7% of placebo-treated subjects that had negative baseline ANA titers developed positive titers at week 24. Two subjects out of 3046 treated with adalimumab developed clinical signs suggestive of new-onset lupus-like syndrome. The subjects improved following discontinuation of therapy. No subjects developed lupus nephritis or central nervous system symptoms. The impact of long-term treatment with adalimumab products on the development of autoimmune diseases is unknown.

Liver Enzyme Elevations

There have been reports of severe hepatic reactions including acute liver failure in subjects receiving TNF-blockers. In controlled Phase 3 trials of adalimumab (40 mg SC every other week) in subjects with RA, PsA, and AS with control period duration ranging from 4 to 104 weeks, ALT elevations ≥3 × ULN occurred in 3.5% of adalimumab-treated subjects and 1.5% of control-treated subjects. Since many of these subjects in these trials were also taking medications that cause liver enzyme elevations (e.g., NSAIDS, MTX), the relationship between adalimumab and the liver enzyme elevations is not clear. In a controlled Phase 3 trial of adalimumab in subjects with polyarticular JIA who were 4 to 17 years, ALT elevations ≥3 × ULN occurred in 4.4% of adalimumab-treated subjects and 1.5% of control-treated subjects (ALT more common than AST); liver enzyme test elevations were more frequent among those treated with the combination of adalimumab and MTX than those treated with adalimumab alone. In general, these elevations did not lead to discontinuation of adalimumab treatment. No ALT elevations ≥3 × ULN occurred in the open-label study of adalimumab in subjects with polyarticular JIA who were 2 to <4 years.

In controlled Phase 3 trials of adalimumab (initial doses of 160 mg and 80 mg, or 80 mg and 40 mg on Days 1 and 15, respectively, followed by 40 mg every other week) in adult subjects with Crohn's Disease with a control period duration ranging from 4 to 52 weeks, ALT elevations ≥3 × ULN occurred in 0.9% of adalimumab-treated subjects and 0.9% of control-treated subjects. In the Phase 3 trial of adalimumab in pediatric subjects with Crohn's disease which evaluated efficacy and safety of two body weight based maintenance dose regimens following body weight based induction therapy up to 52 weeks of treatment, ALT elevations ≥3 × ULN occurred in 2.6% (5/192) of subjects, of whom 4 were receiving concomitant immunosuppressants at baseline; none of these subjects discontinued due to abnormalities in ALT tests. In controlled Phase 3 trials of adalimumab (initial doses of 160 mg and 80 mg on Days 1 and 15 respectively, followed by 40 mg every other week) in adult subjects with UC with control period duration ranging from 1 to 52 weeks, ALT elevations ≥3 × ULN occurred in 1.5% of adalimumab-treated subjects and 1.0% of control-treated subjects. In controlled Phase 3 trials of adalimumab (initial dose of 80 mg then 40 mg every other week) in subjects with Ps with control period duration ranging from 12 to 24 weeks, ALT elevations ≥3 × ULN occurred in 1.8% of adalimumab-treated subjects and 1.8% of control-treated subjects. In controlled trials of adalimumab (initial doses of 160 mg at Week 0 and 80 mg at Week 2, followed by 40 mg every week starting at Week 4), in subjects with HS with a control period duration ranging from 12 to 16 weeks, ALT elevations ≥3 × ULN occurred in 0.3% of adalimumab-treated subjects and 0.6% of control-treated subjects. In controlled trials of adalimumab (initial doses of 80 mg at Week 0 followed by 40 mg every other week starting at Week 1) in adult subjects with uveitis with an exposure of 165.4 PYs and 119.8 PYs in adalimumab-treated and control-treated subjects, respectively, ALT elevations ≥3 × ULN occurred in 2.4% of adalimumab-treated subjects and 2.4% of control-treated subjects.

Other Adverse Reactions

Rheumatoid Arthritis Clinical Studies

The data described below reflect exposure to adalimumab in 2468 subjects, including 2073 exposed for 6 months, 1497 exposed for greater than one year and 1380 in adequate and well-controlled studies (Studies RA-I, RA-II, RA-III, and RA-IV). Adalimumab was studied primarily in placebo-controlled trials and in long-term follow up studies for up to 36 months duration. The population had a mean age of 54 years, 77% were female, 91% were Caucasian and had moderately to severely active rheumatoid arthritis. Most subjects received 40 mg adalimumab every other week [see Clinical Studies (14.1)].

Table 1 summarizes reactions reported at a rate of at least 5% in subjects treated with adalimumab 40 mg every other week compared to placebo and with an incidence higher than placebo. In Study RA-III, the types and frequencies of adverse reactions in the second year open-label extension were similar to those observed in the one-year double-blind portion.

Table 1. Adverse Reactions Reported by ≥5% of Subjects Treated with Adalimumab During Placebo-Controlled Period of Pooled RA Studies (Studies RA-I, RA-II, RA-III, and RA-IV)
 | Adalimumab 40 mg subcutaneous Every Other Week | Placebo
 | (N=705) | (N=690)
Adverse Reaction (Preferred Term)
Respiratory
Upper respiratory infection | 17% | 13%
Sinusitis | 11% | 9%
Flu syndrome | 7% | 6%
Gastrointestinal
Nausea | 9% | 8%
Abdominal pain | 7% | 4%
Laboratory Tests*
Laboratory test abnormal | 8% | 7%
Hypercholesterolemia | 6% | 4%
Hyperlipidemia | 7% | 5%
Hematuria | 5% | 4%
Alkaline phosphatase increased | 5% | 3%
Other
Headache | 12% | 8%
Rash | 12% | 6%
Accidental injury | 10% | 8%
Injection site reaction** | 8% | 1%
Back pain | 6% | 4%
Urinary tract infection | 8% | 5%
Hypertension | 5% | 3%
* Laboratory test abnormalities were reported as adverse reactions in European trials
** Does not include injection site erythema, itching, hemorrhage, pain or swelling

Less Common Adverse Reactions in Rheumatoid Arthritis Clinical Studies

Other infrequent serious adverse reactions that do not appear in the Warnings and Precautions or Adverse Reactions sections that occurred at an incidence of less than 5% in adalimumab-treated subjects in RA studies (RA-I, RA-II, RA-III, and RA-IV) were:

Body As A Whole: Pain in extremity, pelvic pain, surgery, thorax pain

Cardiovascular System: Arrhythmia, atrial fibrillation, chest pain, coronary artery disorder, heart arrest, hypertensive encephalopathy, myocardial infarct, palpitation, pericardial effusion, pericarditis, syncope, tachycardia

Digestive System: Cholecystitis, cholelithiasis, esophagitis, gastroenteritis, gastrointestinal hemorrhage, hepatic necrosis, vomiting

Endocrine System: Parathyroid disorder

Hemic And Lymphatic System: Agranulocytosis, polycythemia

Metabolic And Nutritional Disorders: Dehydration, healing abnormal, ketosis, paraproteinemia, peripheral edema

Musculo-Skeletal System: Arthritis, bone disorder, bone fracture (not spontaneous), bone necrosis, joint disorder, muscle cramps, myasthenia, pyogenic arthritis, synovitis, tendon disorder

Neoplasia: Adenoma

Nervous System: Confusion, paresthesia, subdural hematoma, tremor

Respiratory System: Asthma, bronchospasm, dyspnea, lung function decreased, pleural effusion

Special Senses: Cataract

Thrombosis: Thrombosis leg

Urogenital System: Cystitis, kidney calculus, menstrual disorder

Juvenile Idiopathic Arthritis Clinical Studies

In general, the adverse reactions in the adalimumab-treated subjects in the polyarticular juvenile idiopathic arthritis (JIA) trials (Studies JIA-I and JIA-II) [see Clinical Studies (14.2)] were similar in frequency and type to those seen in adult subjects [see Warnings and Precautions (5), Adverse Reactions (6)]. Important findings and differences from adults are discussed in the following paragraphs.

In Study JIA-I, adalimumab was studied in 171 subjects who were 4 to 17 years of age, with polyarticular JIA. Severe adverse reactions reported in the study included neutropenia, streptococcal pharyngitis, increased aminotransferases, herpes zoster, myositis, metrorrhagia, and appendicitis. Serious infections were observed in 4% of subjects within approximately 2 years of initiation of treatment with adalimumab and included cases of herpes simplex, pneumonia, urinary tract infection, pharyngitis, and herpes zoster.

In Study JIA-I, 45% of subjects experienced an infection while receiving adalimumab with or without concomitant MTX in the first 16 weeks of treatment. The types of infections reported in adalimumab-treated subjects were generally similar to those commonly seen in polyarticular JIA subjects who are not treated with TNF blockers. Upon initiation of treatment, the most common adverse reactions occurring in this population treated with adalimumab were injection site pain and injection site reaction (19% and 16%, respectively). A less commonly reported adverse event in subjects receiving adalimumab was granuloma annulare which did not lead to discontinuation of adalimumab treatment.

In the first 48 weeks of treatment in Study JIA-I, non-serious hypersensitivity reactions were seen in approximately 6% of subjects and included primarily localized allergic hypersensitivity reactions and allergic rash.

In Study JIA-I, 10% of subjects treated with adalimumab who had negative baseline anti-dsDNA antibodies developed positive titers after 48 weeks of treatment. No subject developed clinical signs of autoimmunity during the clinical trial.

Approximately 15% of subjects treated with adalimumab developed mild-to-moderate elevations of creatine phosphokinase (CPK) in Study JIA-I. Elevations exceeding 5 times the upper limit of normal were observed in several subjects. CPK concentrations decreased or returned to normal in all subjects. Most subjects were able to continue adalimumab without interruption.

In Study JIA-II, adalimumab was studied in 32 subjects who were 2 to <4 years of age or 4 years of age and older weighing <15 kg with polyarticular JIA. The safety profile for this population was similar to the safety profile seen in subjects 4 to 17 years of age with polyarticular JIA.

In Study JIA-II, 78% of subjects experienced an infection while receiving adalimumab. These included nasopharyngitis, bronchitis, upper respiratory tract infection, otitis media, and were mostly mild to moderate in severity. Serious infections were observed in 9% of subjects receiving adalimumab in the study and included dental caries, rotavirus gastroenteritis, and varicella.

In Study JIA-II, non-serious allergic reactions were observed in 6% of subjects and included intermittent urticaria and rash, which were all mild in severity.

Psoriatic Arthritis and Ankylosing Spondylitis Clinical Studies

Adalimumab has been studied in 395 subjects with psoriatic arthritis (PsA) in two placebo-controlled trials and in an open label study and in 393 subjects with ankylosing spondylitis (AS) in two placebo-controlled studies [see Clinical Studies (14.3, 14.4)]. The safety profile for subjects with PsA and AS treated with adalimumab 40 mg every other week was similar to the safety profile seen in subjects with RA, adalimumab Studies RA-I through IV.

Crohn's Disease Clinical Studies

Adults: The safety profile of adalimumab in 1478 adult subjects with Crohn's disease from four placebo-controlled and two open-label extension studies [see Clinical Studies (14.5)] was similar to the safety profile seen in subjects with RA.

Pediatric Patients 6 Years to 17 Years: The safety profile of adalimumab in 192 pediatric subjects from one double-blind study (Study PCD-I) and one open-label extension study [see Clinical Studies (14.6)] was similar to the safety profile seen in adult subjects with Crohn's disease.

During the 4-week open label induction phase of Study PCD-I, the most common adverse reactions occurring in the pediatric population treated with adalimumab were injection site pain and injection site reaction (6% and 5%, respectively).

A total of 67% of children experienced an infection while receiving adalimumab in Study PCD-I. These included upper respiratory tract infection and nasopharyngitis.

A total of 5% of children experienced a serious infection while receiving adalimumab in Study PCD-I. These included viral infection, device related sepsis (catheter), gastroenteritis, H1N1 influenza, and disseminated histoplasmosis.

In Study PCD-I, allergic reactions were observed in 5% of children which were all non-serious and were primarily localized reactions.

Ulcerative Colitis Clinical Studies

Adults: The safety profile of adalimumab in 1010 adult subjects with ulcerative colitis (UC) from two placebo-controlled studies and one open-label extension study [see Clinical Studies (14.7)] was similar to the safety profile seen in subjects with RA.

Plaque Psoriasis Clinical Studies

Adalimumab has been studied in 1696 subjects with plaque psoriasis (Ps) in placebo-controlled and open-label extension studies [see Clinical Studies (14.8)]. The safety profile for subjects with Ps treated with adalimumab was similar to the safety profile seen in subjects with RA with the following exceptions. In the placebo-controlled portions of the clinical trials in Ps subjects, adalimumab-treated subjects had a higher incidence of arthralgia when compared to controls (3% vs. 1%).

Hidradenitis Suppurativa Clinical Studies

Adalimumab has been studied in 727 subjects with hidradenitis suppurativa (HS) in three placebo-controlled studies and one open-label extension study [see Clinical Studies (14.9)]. The safety profile for subjects with HS treated with adalimumab weekly was consistent with the known safety profile of adalimumab.

Flare of HS, defined as ≥25% increase from baseline in abscesses and inflammatory nodule counts and with a minimum of 2 additional lesions, was documented in 22 (22%) of the 100 subjects who were withdrawn from adalimumab treatment following the primary efficacy timepoint in two studies.

Uveitis Clinical Studies

Adalimumab has been studied in 464 adult subjects with uveitis (UV) in placebo-controlled and open-label extension studies and in 90 pediatric subjects with uveitis (Study PUV-I) [see Clinical Studies (14.10, 14.11)]. The safety profile for subjects with UV treated with adalimumab was similar to the safety profile seen in subjects with RA.

6.2 Immunogenicity

The observed incidence of anti-drug antibodies is highly dependent on the sensitivity and specificity of the assay. Differences in assay methods preclude meaningful comparisons of the incidence of anti-drug antibodies in the studies described below with the incidence of anti-drug antibodies in other studies, including those of adalimumab or of other adalimumab products.

There are two assays that have been used to measure anti-adalimumab antibodies. With the ELISA, antibodies to adalimumab could be detected only when serum adalimumab concentrations were <2 mcg/mL. The ECL assay can detect anti-adalimumab antibody titers independent of adalimumab concentrations in the serum samples. The incidence of anti-adalimumab antibody (AAA) development in patients treated with adalimumab are presented in Table 2.

Table 2: Anti-Adalimumab Antibody Development Determined by ELISA and ECL Assay in Patients Treated with Adalimumab
Indications |  | Study Duration | Anti-Adalimumab Antibody Incidence by ELISA (n/N) |  | Anti-Adalimumab Antibody Incidence by ECL Assay (n/N)
Indications |  | Study Duration | In all patients who received adalimumab | In patients with serum adalimumab concentrations <2 mcg/mL
Rheumatoid Arthritisa |  | 6 to 12 months | 5% (58/1062) | NR | NA
Juvenile Idiopathic Arthritis (JIA) | 4 to 17 years of ageb | 48 weeks | 16% (27/171) | NR | NA
Juvenile Idiopathic Arthritis (JIA) | 2 to 4 years of age or ≥4 years of age and weighing <15 kg | 24 weeks | 7% (1/15)c | NR | NA
Psoriatic Arthritisd |  | 48 weekse | 13% (24/178) | NR | NA
Ankylosing Spondylitis |  | 24 weeks | 9% (16/185) | NR | NA
Adult Crohn's Disease |  | 56 weeks | 3% (7/269) | 8% (7/86) | NA
Pediatric Crohn's Disease |  | 52 weeks | 3% (6/182) | 10% (6/58) | NA
Adult Ulcerative Colitis |  | 52 weeks | 5% (19/360) | 21% (19/92) | NA
Plaque Psoriasisf |  | Up to 52 weeksg | 8% (77/920) | 21% (77/372) | NA
Hidradenitis Suppurativa |  | 36 weeks | 7% (30/461) | 28% (58/207)h | 61% (272/445)i
Non-infectious Uveitis |  | 52 weeks | 5% (12/249) | 21% (12/57) | 40% (99/249)j
n: number of patients with anti-adalimumab antibody; NR: not reported; NA: Not applicable (not performed)
a In patients receiving concomitant methotrexate (MTX), the incidence of anti-adalimumab antibody was 1% compared to 12% with adalimumab monotherapy
b In patients receiving concomitant MTX, the incidence of anti-adalimumab antibody was 6% compared to 26% with adalimumab monotherapy
c This patient received concomitant MTX
d In patients receiving concomitant MTX, the incidence of antibody development was 7% compared to 1% in RA
e Subjects enrolled after completing 2 previous studies of 24 weeks or 12 weeks of treatments
f In plaque psoriasis patients who were on adalimumab monotherapy and subsequently withdrawn from the treatment, the rate of antibodies to adalimumab after retreatment was similar to the rate observed prior to withdrawal
g One 12-week Phase 2 study and one 52-week Phase 3 study
h Among subjects in the 2 Phase 3 studies who stopped adalimumab treatment for up to 24 weeks and in whom adalimumab serum levels subsequently declined to <2 mcg/mL (approximately 22% of total subjects studied)
i No apparent association between antibody development and safety was observed
j No correlation of antibody development to safety or efficacy outcomes was observed

Rheumatoid Arthritis and Psoriatic Arthritis: Subjects in Studies RA-I, RA-II, and RA-III were tested at multiple time points for antibodies to adalimumab using the ELISA during the 6- to 12-month period. No apparent correlation of antibody development to adverse reactions was observed. With monotherapy, subjects receiving every other week dosing may develop antibodies more frequently than those receiving weekly dosing. In subjects receiving the recommended dosage of 40 mg every other week as monotherapy, the ACR 20 response was lower among antibody-positive subjects than among antibody-negative subjects. The long-term immunogenicity of adalimumab products is unknown.

6.3 Postmarketing Experience

The following adverse reactions have been identified during post-approval use of adalimumab products. Because these reactions are reported voluntarily from a population of uncertain size, it is not always possible to reliably estimate their frequency or establish a causal relationship to adalimumab products exposure.

Gastrointestinal disorders: Diverticulitis, large bowel perforations including perforations associated with diverticulitis and appendiceal perforations associated with appendicitis, pancreatitis

General disorders and administration site conditions: Pyrexia

Hepato-biliary disorders: Liver failure, hepatitis, autoimmune hepatitis

Immune system disorders: Sarcoidosis

Neoplasms benign, malignant and unspecified (including cysts and polyps): Merkel Cell Carcinoma (neuroendocrine carcinoma of the skin)

Nervous system disorders: Demyelinating disorders (e.g., optic neuritis, Guillain-Barré syndrome), cerebrovascular accident

Respiratory disorders: Interstitial lung disease, including pulmonary fibrosis, pulmonary embolism

Skin reactions: Stevens Johnson Syndrome, cutaneous vasculitis, erythema multiforme, new or worsening psoriasis (all sub-types including pustular and palmoplantar), alopecia, lichenoid skin reaction

Vascular disorders: Systemic vasculitis, deep vein thrombosis

7 DRUG INTERACTIONS

7.1 Methotrexate

Adalimumab has been studied in rheumatoid arthritis (RA) patients taking concomitant methotrexate (MTX). Although MTX reduced the apparent clearance of adalimumab, the data do not suggest the need for dose adjustment of either Adalimumab-adbm or MTX [see Clinical Pharmacology (12.3)].

7.2 Biological Products

In clinical studies in patients with RA, an increased risk of serious infections has been observed with the combination of TNF blockers with anakinra or abatacept, with no added benefit; therefore, use of Adalimumab-adbm with abatacept or anakinra is not recommended in patients with RA [see Warnings and Precautions (5.7, 5.11)]. A higher rate of serious infections has also been observed in patients with RA treated with rituximab who received subsequent treatment with a TNF blocker. There is insufficient information regarding the concomitant use of Adalimumab-adbm and other biologic products for the treatment of RA, PsA, AS, CD, UC, Ps, HS and UV. Concomitant administration of Adalimumab-adbm with other biologic DMARDs (e.g., anakinra and abatacept) or other TNF blockers is not recommended based upon the possible increased risk for infections and other potential pharmacological interactions.

7.3 Live Vaccines

Avoid the use of live vaccines with Adalimumab-adbm [see Warnings and Precautions (5.10)].

7.4 Cytochrome P450 Substrates

The formation of CYP450 enzymes may be suppressed by increased concentrations of cytokines (e.g., TNFα, IL-6) during chronic inflammation. It is possible for products that antagonize cytokine activity, such as adalimumab products, to influence the formation of CYP450 enzymes. Upon initiation or discontinuation of Adalimumab-adbm in patients being treated with CYP450 substrates with a narrow therapeutic index, monitoring of the effect (e.g., warfarin) or drug concentration (e.g., cyclosporine or theophylline) is recommended and the individual dose of the drug product may be adjusted as needed.

8 USE IN SPECIFIC POPULATIONS

8.1 Pregnancy

Risk Summary

Available studies with use of adalimumab during pregnancy do not reliably establish an association between adalimumab and major birth defects. Clinical data are available from the Organization of Teratology Information Specialists (OTIS)/MotherToBaby Pregnancy Registry in pregnant women with rheumatoid arthritis (RA) or Crohn's disease (CD) treated with adalimumab. Registry results showed a rate of 10% for major birth defects with first trimester use of adalimumab in pregnant women with RA or CD and a rate of 7.5% for major birth defects in the disease-matched comparison cohort. The lack of pattern of major birth defects is reassuring and differences between exposure groups may have impacted the occurrence of birth defects (see Data).

Adalimumab is actively transferred across the placenta during the third trimester of pregnancy and may affect immune response in the in-utero exposed infant (see Clinical Considerations). In an embryo-fetal perinatal development study conducted in cynomolgus monkeys, no fetal harm or malformations were observed with intravenous administration of adalimumab during organogenesis and later in gestation, at doses that produced exposures up to approximately 373 times the maximum recommended human dose (MRHD) of 40 mg subcutaneous without methotrexate (see Data).

The estimated background risk of major birth defects and miscarriage for the indicated populations is unknown. All pregnancies have a background risk of birth defect, loss, or other adverse outcomes. In the U.S. general population, the estimated background risk of major birth defects and miscarriage in clinically recognized pregnancies is 2-4% and 15-20%, respectively.

Clinical Considerations

Disease-associated maternal and embryo/fetal risk

Published data suggest that the risk of adverse pregnancy outcomes in women with RA or inflammatory bowel disease (IBD) is associated with increased disease activity. Adverse pregnancy outcomes include preterm delivery (before 37 weeks of gestation), low birth weight (less than 2500 g) infants, and small for gestational age at birth.

Fetal/Neonatal Adverse Reactions

Monoclonal antibodies are increasingly transported across the placenta as pregnancy progresses, with the largest amount transferred during the third trimester (see Data). Risks and benefits should be considered prior to administering live or live-attenuated vaccines to infants exposed to adalimumab products in utero [see Use in Specific Populations (8.4)].

Data

Human Data

A prospective cohort pregnancy exposure registry conducted by OTIS/MotherToBaby in the U.S. and Canada between 2004 and 2016 compared the risk of major birth defects in live-born infants of 221 women (69 RA, 152 CD) treated with adalimumab during the first trimester and 106 women (74 RA, 32 CD) not treated with adalimumab.

The proportion of major birth defects among live-born infants in the adalimumab-treated and untreated cohorts was 10% (8.7% RA, 10.5% CD) and 7.5% (6.8% RA, 9.4% CD), respectively. The lack of pattern of major birth defects is reassuring and differences between exposure groups may have impacted the occurrence of birth defects. This study cannot reliably establish whether there is an association between adalimumab and major birth defects because of methodological limitations of the registry, including small sample size, the voluntary nature of the study, and the non-randomized design.

In an independent clinical study conducted in ten pregnant women with IBD treated with adalimumab, adalimumab concentrations were measured in maternal serum as well as in cord blood (n=10) and infant serum (n=8) on the day of birth. The last dose of adalimumab was given between 1 and 56 days prior to delivery. Adalimumab concentrations were 0.16-19.7 mcg/mL in cord blood, 4.28-17.7 mcg/mL in infant serum, and 0-16.1 mcg/mL in maternal serum. In all but one case, the cord blood concentration of adalimumab was higher than the maternal serum concentration, suggesting adalimumab actively crosses the placenta. In addition, one infant had serum concentrations at each of the following: 6 weeks (1.94 mcg/mL), 7 weeks (1.31 mcg/mL), 8 weeks (0.93 mcg/mL), and 11 weeks (0.53 mcg/mL), suggesting adalimumab can be detected in the serum of infants exposed in utero for at least 3 months from birth.

Animal Data

In an embryo-fetal perinatal development study, pregnant cynomolgus monkeys received adalimumab from gestation days 20 to 97 at doses that produced exposures up to 373 times that achieved with the MRHD without methotrexate (on an AUC basis with maternal IV doses up to 100 mg/kg/week). Adalimumab did not elicit harm to the fetuses or malformations.

8.2 Lactation

Risk Summary

Limited data from case reports in the published literature describe the presence of adalimumab in human milk at infant doses of 0.1% to 1% of the maternal serum concentration. Published data suggest that the systemic exposure to a breastfed infant is expected to be low because adalimumab is a large molecule and is degraded in the gastrointestinal tract. However, the effects of local exposure in the gastrointestinal tract are unknown. There are no reports of adverse effects of adalimumab products on the breastfed infant and no effects on milk production. The developmental and health benefits of breastfeeding should be considered along with the mother's clinical need for Adalimumab-adbm and any potential adverse effects on the breastfed child from Adalimumab-adbm or from the underlying maternal condition.

8.4 Pediatric Use

The safety and effectiveness of Adalimumab-adbm have not been established in pediatric patients with psoriatic arthritis, ankylosing spondylitis, or plaque psoriasis.

The safety and effectiveness of Adalimumab-adbm have been established for:

- reducing signs and symptoms of moderately to severely active polyarticular JIA in pediatric patients 2 years of age and older.
- the treatment of moderately to severely active Crohn's disease in pediatric patients 6 years of age and older.
- the treatment of moderate to severe hidradenitis suppurativa in patients 12 years of age and older.
- the treatment of non-infectious intermediate, posterior, and panuveitis in pediatric patients 2 years of age and older.

A pediatric assessment for Adalimumab-adbm demonstrates that Adalimumab-adbm is safe and effective for pediatric patients in an indication for which Humira (adalimumab) is approved. However, Adalimumab-adbm is not approved for such indication due to marketing exclusivity for Humira (adalimumab).

Due to their inhibition of TNFα, adalimumab products administered during pregnancy could affect immune response in the in utero-exposed newborn and infant. Data from eight infants exposed to adalimumab in utero suggest adalimumab crosses the placenta [see Use in Specific Populations (8.1)]. The clinical significance of elevated adalimumab concentrations in infants is unknown. The safety of administering live or live-attenuated vaccines in exposed infants is unknown. Risks and benefits should be considered prior to vaccinating (live or live-attenuated) exposed infants.

Post-marketing cases of lymphoma, including hepatosplenic T-cell lymphoma and other malignancies, some fatal, have been reported among children, adolescents, and young adults who received treatment with TNF-blockers including adalimumab products [see Warnings and Precautions (5.2)].

Juvenile Idiopathic Arthritis

The safety and effectiveness of Adalimumab-adbm for the treatment of moderately to severely active polyarticular JIA have been established in pediatric patients 2 years of age and older. Use for this indication is supported by evidence from an adequate and well-controlled study (Study JIA) of adalimumab in patients 4 to 17 years of age [see Clinical Studies (14.2)] and a safety study (Study JIA-II) of adalimumab in patients 2 to <4 years of age where the safety profile was similar to patients 4 to 17 years of age [see Adverse Reactions (6.1)]. Adalimumab products have not been studied in patients with polyarticular JIA less than 2 years of age or in patients with a weight below 10 kg.

The safety of adalimumab in pediatric patients in the polyarticular JIA trials was generally similar to that observed in adults with certain exceptions [see Adverse Reactions (6.1)].

The safety and effectiveness of Adalimumab-adbm have not been established in pediatric patients with JIA less than 2 years of age.

Pediatric Crohn's Disease

The safety and effectiveness of Adalimumab-adbm for the treatment of moderately to severely active Crohn's disease have been established in pediatric patients 6 years of age and older. Use of Adalimumab-adbm for this indication is supported by evidence from adequate and well-controlled studies in adults with additional data from a randomized, double-blind, 52-week clinical study of two dose concentrations of adalimumab in 192 pediatric patients (6 years to 17 years of age) [see Adverse Reactions (6.1), Clinical Pharmacology (12.2, 12.3), Clinical Studies (14.6)]. The adverse reaction profile in patients 6 years to 17 years of age was similar to adults.

The safety and effectiveness of Adalimumab-adbm have not been established in pediatric patients with Crohn's disease less than 6 years of age.

Pediatric Uveitis

The safety and effectiveness of Adalimumab-adbm for the treatment of non-infectious, intermediate, posterior, and panuveitis have been established in pediatric patients 2 years of age and older. Use of Adalimumab-adbm for this indication is supported by evidence from adequate and well-controlled studies of adalimumab in adults and a 2:1 randomized, controlled clinical study of adalimumab in 90 pediatric patients [see Clinical Studies (14.11)]. The safety and effectiveness of Adalimumab-adbm have not been established in pediatric patients with uveitis less than 2 years of age.

Hidradenitis Suppurativa

Use of Adalimumab-adbm in pediatric patients 12 years of age and older for the treatment of moderate to severe HS is supported by evidence from adequate and well-controlled studies of adalimumab in adult HS patients. Additional population pharmacokinetic modeling and simulation predicted that weight-based dosing of adalimumab in pediatric patients 12 years of age and older can provide generally similar exposure to adult HS patients. The course of HS is sufficiently similar in adult and adolescent patients to allow extrapolation of data from adult to adolescent patients. The recommended dosage in pediatric patients 12 years of age or older is based on body weight [see Dosage and Administration (2.7), Clinical Pharmacology (12.3), and Clinical Studies (14.9)].

The safety and effectiveness of Adalimumab-adbm have not been established in patients less than 12 years of age with HS.

8.5 Geriatric Use

In clinical studies of RA (Studies RA-I, RA-II, RA-III, and RA-IV), a total of 519 subjects 65 years of age and older, including 107 subjects 75 years of age and older, received adalimumab. No overall difference in effectiveness was observed between these subjects and younger adult subjects.

The frequency of serious infection and malignancy among adalimumab-treated subjects 65 years of age and older was higher than for those less than 65 years of age. Consider the benefits and risks of Adalimumab-adbm in patients 65 years of age and older. In patients treated with Adalimumab-adbm, closely monitor for the development of infection or malignancy [see Warnings and Precautions (5.1, 5.2)].

10 OVERDOSAGE

Doses up to 10 mg/kg have been administered to patients in clinical trials without evidence of dose-limiting toxicities. In case of overdosage, it is recommended that the patient be monitored for any signs or symptoms of adverse reactions or effects and appropriate symptomatic treatment instituted immediately.

Consider contacting the Poison Help line (1-800-222-1222) or medical toxicologist for additional overdose management recommendations.

11 DESCRIPTION

Adalimumab-adbm is a tumor necrosis factor blocker. Adalimumab-adbm is a recombinant human IgG1 monoclonal antibody produced by recombinant DNA technology in a mammalian cell (Chinese Hamster Ovary (CHO)) expression system and is purified by a process that includes specific viral inactivation and removal steps. It consists of 1330 amino acids and has a molecular weight of approximately 148 kilodaltons.

Adalimumab-adbm injection is supplied as a sterile, preservative-free solution of adalimumab-adbm for subcutaneous administration. The drug product is supplied as either a single-dose, prefilled pen (Adalimumab-adbm Pen) or as a single-dose, 1 mL prefilled glass syringe. Enclosed within the pen is a single-dose, 1 mL prefilled glass syringe. The solution of Adalimumab-adbm is clear to slightly opalescent and colorless to slightly yellow, with a pH of about 5.5.

Each 40 mg/0.4 mL prefilled syringe or prefilled pen delivers 0.4 mL (40 mg) of drug product. Each 0.4 mL of Adalimumab-adbm contains adalimumab-adbm (40 mg), glacial acetic acid (0.03 mg), polysorbate 80 (0.2 mg), sodium acetate trihydrate (0.47 mg), trehalose dihydrate (30.3 mg), and Water for Injection, USP.

Each 40 mg/0.8 mL prefilled syringe or prefilled pen delivers 0.8 mL (40 mg) of drug product. Each 0.8 mL of Adalimumab-adbm contains adalimumab-adbm (40 mg), glacial acetic acid (0.13 mg), polysorbate 80 (0.8 mg), sodium acetate trihydrate (2.4 mg), trehalose dihydrate (65.0 mg), and Water for Injection, USP.

Each 20 mg/0.4 mL prefilled syringe delivers 0.4 mL (20 mg) of drug product. Each 0.4 mL of Adalimumab-adbm contains adalimumab-adbm (20 mg), glacial acetic acid (0.06 mg), polysorbate 80 (0.4 mg), sodium acetate trihydrate (1.21 mg), trehalose dihydrate (32.5 mg), and Water for Injection, USP.

Each 10 mg/0.2 mL prefilled syringe delivers 0.2 mL (10 mg) of drug product. Each 0.2 mL of Adalimumab-adbm contains adalimumab-adbm (10 mg), glacial acetic acid (0.03 mg), polysorbate 80 (0.2 mg), sodium acetate trihydrate (0.61 mg), trehalose dihydrate (16.3 mg), and Water for Injection, USP.

12 CLINICAL PHARMACOLOGY

12.1 Mechanism of Action

Adalimumab products bind specifically to TNF-alpha and block its interaction with the p55 and p75 cell surface TNF receptors. Adalimumab products also lyse surface TNF expressing cells in vitro in the presence of complement. Adalimumab products do not bind or inactivate lymphotoxin (TNF-beta). TNF is a naturally occurring cytokine that is involved in normal inflammatory and immune responses. Elevated concentrations of TNF are found in the synovial fluid of patients with RA, JIA, PsA, and AS and play an important role in both the pathologic inflammation and the joint destruction that are hallmarks of these diseases. Increased concentrations of TNF are also found in psoriasis plaques. In Ps, treatment with Adalimumab-adbm may reduce the epidermal thickness and infiltration of inflammatory cells. The relationship between these pharmacodynamic activities and the mechanism(s) by which adalimumab products exert their clinical effects is unknown.

Adalimumab products also modulate biological responses that are induced or regulated by TNF, including changes in the concentrations of adhesion molecules responsible for leukocyte migration (ELAM-1, VCAM-1, and ICAM-1 with an IC50 of 1-2 × 10^-10M).

12.2 Pharmacodynamics

After treatment with adalimumab, a decrease in concentrations of acute phase reactants of inflammation (C-reactive protein [CRP] and erythrocyte sedimentation rate [ESR]) and serum cytokines (IL-6) was observed compared to baseline in patients with rheumatoid arthritis. A decrease in CRP concentrations was also observed in patients with Crohn's disease, ulcerative colitis and hidradenitis suppurativa. Serum concentrations of matrix metalloproteinases (MMP-1 and MMP-3) that produce tissue remodeling responsible for cartilage destruction were also decreased after adalimumab administration.

12.3 Pharmacokinetics

The pharmacokinetics of adalimumab were linear over the dose range of 0.5 to 10 mg/kg following administration of a single intravenous dose (adalimumab products are not approved for intravenous use). Following 20, 40, and 80 mg every other week and every week subcutaneous administration, adalimumab mean serum trough concentrations at steady state increased approximately proportionally with dose in RA patients. The mean terminal half-life was approximately 2 weeks, ranging from 10 to 20 days across studies. Healthy subjects and patients with RA displayed similar adalimumab pharmacokinetics.

Adalimumab exposure in patients treated with 80 mg every other week is estimated to be comparable with that in patients treated with 40 mg every week.

Absorption

The average absolute bioavailability of adalimumab following a single 40 mg subcutaneous dose was 64%. The mean time to reach the maximum concentration was 5.5 days (131 ± 56 hours) and the maximum serum concentration was 4.7 ± 1.6 mcg/mL in healthy subjects following a single 40 mg subcutaneous administration of adalimumab.

Distribution

The distribution volume (Vss) ranged from 4.7 to 6.0 L following intravenous administration of doses ranging from 0.25 to 10 mg/kg in RA patients.

Elimination

The single dose pharmacokinetics of adalimumab in RA patients were determined in several studies with intravenous doses ranging from 0.25 to 10 mg/kg. The systemic clearance of adalimumab is approximately 12 mL/hr. In long-term studies with dosing more than two years, there was no evidence of changes in clearance over time in RA patients.

Patient Population

Rheumatoid Arthritis and Ankylosing Spondylitis: In patients receiving 40 mg adalimumab every other week, adalimumab mean steady-state trough concentrations were approximately 5 mcg/mL and 8 to 9 mcg/mL, without and with MTX concomitant treatment, respectively. Adalimumab concentrations in the synovial fluid from five rheumatoid arthritis patients ranged from 31 to 96% of those in serum. The pharmacokinetics of adalimumab in patients with AS were similar to those in patients with RA.

Psoriatic Arthritis: In patients receiving 40 mg every other week, adalimumab mean steady-state trough concentrations were 6 to 10 mcg/mL and 8.5 to 12 mcg/mL, without and with MTX concomitant treatment, respectively.

Plaque Psoriasis: Adalimumab mean steady-state trough concentration was approximately 5 to 6 mcg/mL during 40 mg adalimumab every other week treatment.

Adult Uveitis: Adalimumab mean steady concentration was approximately 8 to 10 mcg/mL during adalimumab 40 mg every other week treatment.

Adult Hidradenitis Suppurativa: Adalimumab trough concentrations were approximately 7 to 8 mcg/mL at Week 2 and Week 4, respectively, after receiving 160 mg on Week 0 followed by 80 mg on Week 2. Mean steady-state trough concentrations at Week 12 through Week 36 were approximately 7 to 11 mcg/mL during adalimumab 40 mg every week treatment.

Adult Crohn's Disease: Adalimumab mean trough concentrations were approximately 12 mcg/mL at Week 2 and Week 4 after receiving 160 mg on Week 0 followed by 80 mg on Week 2. Mean steady-state trough concentrations were 7 mcg/mL at Week 24 and Week 56 during 40 mg adalimumab every other week treatment.

Adult Ulcerative Colitis: Adalimumab mean trough concentrations were approximately 12 mcg/mL at Week 2 and Week 4 after receiving 160 mg on Week 0 followed by 80 mg on Week 2. Mean steady-state trough concentrations were approximately 8 mcg/mL and 15 mcg/mL at Week 52 after receiving a dose of 40 mg adalimumab every other week and 40 mg every week, respectively.

Anti-Drug Antibody Effects on Pharmacokinetics

Rheumatoid Arthritis: A trend toward higher apparent clearance of adalimumab in the presence of anti-adalimumab antibodies was identified.

Hidradenitis Suppurativa: In subjects with moderate to severe HS, antibodies to adalimumab were associated with reduced serum adalimumab concentrations. In general, the extent of reduction in serum adalimumab concentrations is greater with increasing titers of antibodies to adalimumab.

Specific Populations

Geriatric Patients: A lower clearance with increasing age was observed in patients with RA aged 40 to >75 years.

Pediatric Patients:

Juvenile Idiopathic Arthritis:

- 4 years to 17 years of age: The adalimumab mean steady-state trough concentrations were 6.8 mcg/mL and 10.9 mcg/mL in patients weighing <30 kg receiving 20 mg adalimumab subcutaneously every other week as monotherapy or with concomitant MTX, respectively. The adalimumab mean steady-state trough concentrations were 6.6 mcg/mL and 8.1 mcg/mL in patients weighing ≥30 kg receiving 40 mg adalimumab subcutaneously every other week as monotherapy or with MTX concomitant treatment, respectively.
- 2 years to <4 years of age or 4 years of age and older weighing <15 kg: The adalimumab mean steady-state trough adalimumab concentrations were 6.0 mcg/mL and 7.9 mcg/mL in patients receiving adalimumab subcutaneously every other week as monotherapy or with MTX concomitant treatment, respectively.

Pediatric Hidradenitis Suppurativa: Adalimumab concentrations in adolescent patients with HS receiving the recommended dosage regimens are predicted to be similar to those observed in adult subjects with HS based on population pharmacokinetic modeling and simulation.

Pediatric Crohn's Disease: Adalimumab mean ± SD concentrations were 15.7±6.5 mcg/mL at Week 4 following 160 mg at Week 0 and 80 mg at Week 2, and 10.5±6.0 mcg/mL at Week 52 following 40 mg every other week dosing in patients weighing ≥40 kg. Adalimumab mean ± SD concentrations were 10.6±6.1 mcg/mL at Week 4 following dosing 80 mg at Week 0 and 40 mg at Week 2, and 6.9±3.6 mcg/mL at Week 52 following 20 mg every other week dosing in patients weighing <40 kg.

Male and Female Patients: No gender-related pharmacokinetic differences were observed after correction for a patient's body weight. Healthy subjects and patients with rheumatoid arthritis displayed similar adalimumab pharmacokinetics.

Patients with Renal or Hepatic Impairment: No pharmacokinetic data are available in patients with hepatic or renal impairment.

Rheumatoid factor or CRP concentrations: Minor increases in apparent clearance were predicted in RA patients receiving doses lower than the recommended dose and in RA patients with high rheumatoid factor or CRP concentrations. These increases are not likely to be clinically important.

Drug Interaction Studies:

Methotrexate: MTX reduced adalimumab apparent clearance after single and multiple dosing by 29% and 44% respectively, in patients with RA [see Drug Interactions (7.1)].

13 NONCLINICAL TOXICOLOGY

13.1 Carcinogenesis, Mutagenesis, Impairment of Fertility

Long-term animal studies of adalimumab products have not been conducted to evaluate the carcinogenic potential or its effect on fertility.

14 CLINICAL STUDIES

14.1 Clinical Studies in Rheumatoid Arthritis

The efficacy and safety of adalimumab were assessed in five randomized, double-blind studies in subjects ≥18 years of age with active rheumatoid arthritis (RA) diagnosed according to American College of Rheumatology (ACR) criteria. Subjects had at least 6 swollen and 9 tender joints. Adalimumab was administered subcutaneously in combination with methotrexate (MTX) (12.5 to 25 mg, Studies RA-I, RA-III and RA-V) or as monotherapy (Studies RA-II and RA-V) or with other disease-modifying anti-rheumatic drugs (DMARDs) (Study RA-IV).

Study RA-I evaluated 271 subjects who had failed therapy with at least one but no more than four DMARDs and had inadequate response to MTX. Doses of 20, 40 or 80 mg of adalimumab or placebo were given every other week for 24 weeks.

Study RA-II evaluated 544 subjects who had failed therapy with at least one DMARD. Doses of placebo, 20 or 40 mg of adalimumab were given as monotherapy every other week or weekly for 26 weeks.

Study RA-III evaluated 619 subjects who had an inadequate response to MTX. Subjects received placebo, 40 mg of adalimumab every other week with placebo injections on alternate weeks, or 20 mg of adalimumab weekly for up to 52 weeks. Study RA-III had an additional primary endpoint at 52 weeks of inhibition of disease progression (as detected by X-ray results). Upon completion of the first 52 weeks, 457 subjects enrolled in an open-label extension phase in which 40 mg of adalimumab was administered every other week for up to 5 years.

Study RA-IV assessed safety in 636 subjects who were either DMARD-naïve or were permitted to remain on their pre-existing rheumatologic therapy provided that therapy was stable for a minimum of 28 days. Subjects were randomized to 40 mg of adalimumab or placebo every other week for 24 weeks.

Study RA-V evaluated 799 subjects with moderately to severely active RA of less than 3 years duration who were ≥18 years old and MTX naïve. Subjects were randomized to receive either MTX (optimized to 20 mg/week by week 8), adalimumab 40 mg every other week or adalimumab/MTX combination therapy for 104 weeks. Subjects were evaluated for signs and symptoms, and for radiographic progression of joint damage. The median disease duration among subjects enrolled in the study was 5 months. The median MTX dose achieved was 20 mg.

Clinical Response

The percent of adalimumab treated subjects achieving ACR 20, 50 and 70 responses in Studies RA-II and III are shown in Table 3.

Table 3. ACR Responses in Studies RA-II and RA-III (Percent of Subjects)
 | Study RA-II Monotherapy (26 weeks) |  |  | Study RA-III Methotrexate Combination (24 and 52 weeks)
Response | Placebo | Adalimumab | Adalimumab | Placebo/MTX | Adalimumab/MTX
 |  | 40 mg every other week | 40 mg weekly |  | 40 mg every other week
 | N=110 | N=113 | N=103 | N=200 | N=207
ACR20
Month 6 | 19% | 46%* | 53%* | 30% | 63%*
Month 12 | NA | NA | NA | 24% | 59%*
ACR50
Month 6 | 8% | 22%* | 35%* | 10% | 39%*
Month 12 | NA | NA | NA | 10% | 42%*
ACR70
Month 6 | 2% | 12%* | 18%* | 3% | 21%*
Month 12 | NA | NA | NA | 5% | 23%*
* p<0.01, adalimumab vs. placebo

The results of Study RA-I were similar to Study RA-III; subjects receiving adalimumab 40 mg every other week in Study RA-I also achieved ACR 20, 50 and 70 response rates of 65%, 52% and 24%, respectively, compared to placebo responses of 13%, 7% and 3% respectively, at 6 months (p<0.01).

The results of the components of the ACR response criteria for Studies RA-II and RA-III are shown in Table 4. ACR response rates and improvement in all components of ACR response were maintained to week 104. Over the 2 years in Study RA-III, 20% of adalimumab subjects receiving 40 mg every other week achieved a major clinical response, defined as maintenance of an ACR 70 response over a 6-month period. ACR responses were maintained in similar proportions of subjects for up to 5 years with continuous adalimumab treatment in the open-label portion of Study RA-III.

Table 4. Components of ACR Response in Studies RA-II and RA-III
 | Study RA-II |  |  |  | Study RA-III
Parameter (median) | Placebo N=110 |  | Adalimumaba N=113 |  | Placebo/MTX N=200 |  | Adalimumaba/MTX N=207
 | Baseline | Wk 26 | Baseline | Wk 26 | Baseline | Wk 24 | Baseline | Wk 24
Number of tender joints (0-68) | 35 | 26 | 31 | 16* | 26 | 15 | 24 | 8*
Number of swollen joints (0-66) | 19 | 16 | 18 | 10* | 17 | 11 | 18 | 5*
Physician global assessmentb | 7.0 | 6.1 | 6.6 | 3.7* | 6.3 | 3.5 | 6.5 | 2.0*
Patient global assessmentb | 7.5 | 6.3 | 7.5 | 4.5* | 5.4 | 3.9 | 5.2 | 2.0*
Painb | 7.3 | 6.1 | 7.3 | 4.1* | 6.0 | 3.8 | 5.8 | 2.1*
Disability index (HAQ)c | 2.0 | 1.9 | 1.9 | 1.5* | 1.5 | 1.3 | 1.5 | 0.8*
CRP (mg/dL) | 3.9 | 4.3 | 4.6 | 1.8* | 1.0 | 0.9 | 1.0 | 0.4*
a 40 mg adalimumab administered every other week
b Visual analogue scale; 0 = best, 10 = worst
c Disability Index of the Health Assessment Questionnaire; 0 = best, 3 = worst, measures the patient's ability to perform the following: dress/groom, arise, eat, walk, reach, grip, maintain hygiene, and maintain daily activity
* p<0.001, adalimumab vs. placebo, based on mean change from baseline

The time course of ACR 20 response for Study RA-III is shown in Figure 1.

In Study RA-III, 85% of subjects with ACR 20 responses at week 24 maintained the response at 52 weeks. The time course of ACR 20 response for Study RA-I and Study RA-II were similar.

Figure 1. Study RA-III ACR 20 Responses over 52 Weeks

In Study RA-IV, 53% of subjects treated with adalimumab 40 mg every other week plus standard of care had an ACR 20 response at week 24 compared to 35% on placebo plus standard of care (p<0.001). No unique adverse reactions related to the combination of adalimumab and other DMARDs were observed.

In Study RA-V with MTX naïve subjects with recent onset RA, the combination treatment with adalimumab plus MTX led to greater percentages of subjects achieving ACR responses than either MTX monotherapy or adalimumab monotherapy at Week 52 and responses were sustained at Week 104 (see Table 5).

Table 5. ACR Response in Study RA-V (Percent of Subjects)
Response | MTXb N=257 | Adalimumabc N=274 | Adalimumab/MTX N=268
ACR20
Week 52 | 63% | 54% | 73%
Week 104 | 56% | 49% | 69%
ACR50
Week 52 | 46% | 41% | 62%
Week 104 | 43% | 37% | 59%
ACR70
Week 52 | 27% | 26% | 46%
Week 104 | 28% | 28% | 47%
Major Clinical Responsea | 28% | 25% | 49%
a Major clinical response is defined as achieving an ACR70 response for a continuous six-month period
b p<0.05, adalimumab/MTX vs. MTX for ACR 20
p<0.001, adalimumab/MTX vs. MTX for ACR 50 and 70, and Major Clinical Response
c p<0.001, adalimumab/MTX vs. adalimumab

At Week 52, all individual components of the ACR response criteria for Study RA-V improved in the adalimumab/MTX group and improvements were maintained to Week 104.

Radiographic Response

In Study RA-III, structural joint damage was assessed radiographically and expressed as change in Total Sharp Score (TSS) and its components, the erosion score and Joint Space Narrowing (JSN) score, at month 12 compared to baseline. At baseline, the median TSS was approximately 55 in the placebo and 40 mg every other week groups. The results are shown in Table 6. Adalimumab/MTX treated subjects demonstrated less radiographic progression than subjects receiving MTX alone at 52 weeks.

Table 6. Radiographic Mean Changes Over 12 Months in Study RA-III
 | Placebo/MTX | Adalimumab/MTX 40 mg every other week | Placebo/MTX- Adalimumab/MTX (95% Confidence Interval*) | P-value**
Total Sharp score | 2.7 | 0.1 | 2.6 (1.4, 3.8) | <0.001
Erosion score | 1.6 | 0.0 | 1.6 (0.9, 2.2) | <0.001
JSN score | 1.0 | 0.1 | 0.9 (0.3, 1.4) | 0.002
*95% confidence intervals for the differences in change scores between MTX and adalimumab.
**Based on rank analysis

In the open-label extension of Study RA-III, 77% of the original subjects treated with any dose of adalimumab were evaluated radiographically at 2 years. Subjects maintained inhibition of structural damage, as measured by the TSS. Fifty-four percent had no progression of structural damage as defined by a change in the TSS of zero or less. Fifty-five percent (55%) of subjects originally treated with 40 mg adalimumab every other week have been evaluated radiographically at 5 years. Subjects had continued inhibition of structural damage with 50% showing no progression of structural damage defined by a change in the TSS of zero or less.

In Study RA-V, structural joint damage was assessed as in Study RA-III. Greater inhibition of radiographic progression, as assessed by changes in TSS, erosion score and JSN was observed in the adalimumab/MTX combination group as compared to either the MTX or adalimumab monotherapy group at Week 52 as well as at Week 104 (see Table 7).

Table 7. Radiographic Mean Change* in Study RA-V
 |  | MTXa N=257 | Adalimumaba,b N=274 | Adalimumab/MTX N=268
52 Weeks | Total Sharp score | 5.7 (4.2, 7.3) | 3.0 (1.7, 4.3) | 1.3 (0.5, 2.1)
 | Erosion score | 3.7 (2.7, 4.8) | 1.7 (1.0, 2.4) | 0.8 (0.4, 1.2)
 | JSN score | 2.0 (1.2, 2.8) | 1.3 (0.5, 2.1) | 0.5 (0.0, 1.0)
104 Weeks | Total Sharp score | 10.4 (7.7, 13.2) | 5.5 (3.6, 7.4) | 1.9 (0.9, 2.9)
 | Erosion score | 6.4 (4.6, 8.2) | 3.0 (2.0, 4.0) | 1.0 (0.4, 1.6)
 | JSN score | 4.1 (2.7, 5.4) | 2.6 (1.5, 3.7) | 0.9 (0.3, 1.5)
* mean (95% confidence interval)
a p<0.001, adalimumab/MTX vs. MTX at 52 and 104 weeks and for adalimumab/MTX vs. adalimumab at 104 weeks
b p<0.01, for adalimumab/MTX vs. adalimumab at 52 weeks

Physical Function Response

In studies RA-I through IV, adalimumab showed significantly greater improvement than placebo in the disability index of Health Assessment Questionnaire (HAQ-DI) from baseline to the end of study, and significantly greater improvement than placebo in the health-outcomes as assessed by The Short Form Health Survey (SF 36). Improvement was seen in both the Physical Component Summary (PCS) and the Mental Component Summary (MCS).

In Study RA-III, the mean (95% CI) improvement in HAQ-DI from baseline at week 52 was 0.60 (0.55, 0.65) for the adalimumab subjects and 0.25 (0.17, 0.33) for placebo/MTX (p<0.001) subjects. Sixty-three percent of adalimumab-treated subjects achieved a 0.5 or greater improvement in HAQ-DI at week 52 in the double-blind portion of the study. Eighty-two percent of these subjects maintained that improvement through week 104 and a similar proportion of subjects maintained this response through week 260 (5 years) of open-label treatment. Mean improvement in the SF-36 was maintained through the end of measurement at week 156 (3 years).

In Study RA-V, the HAQ-DI and the physical component of the SF-36 showed greater improvement (p<0.001) for the adalimumab/MTX combination therapy group versus either the MTX monotherapy or the adalimumab monotherapy group at Week 52, which was maintained through Week 104.

14.2 Clinical Studies in Juvenile Idiopathic Arthritis

The safety and efficacy of adalimumab was assessed in two studies (Studies JIA-I and JIA-II) in subjects with active polyarticular juvenile idiopathic arthritis (JIA).

Study JIA-I

The safety and efficacy of adalimumab were assessed in a multicenter, randomized, withdrawal, double-blind, parallel-group study in 171 subjects who were 4 to 17 years of age with polyarticular JIA. In the study, the subjects were stratified into two groups: MTX-treated or non-MTX-treated. All subjects had to show signs of active moderate or severe disease despite previous treatment with NSAIDs, analgesics, corticosteroids, or DMARDs. Subjects who received prior treatment with any biologic DMARDs were excluded from the study.

The study included four phases: an open-label lead in phase (OL-LI; 16 weeks), a double-blind randomized withdrawal phase (DB; 32 weeks), an open-label extension phase (OLE-BSA; up to 136 weeks), and an open-label fixed dose phase (OLE-FD; 16 weeks). In the first three phases of the study, adalimumab was administered based on body surface area at a dose of 24 mg/m^2 up to a maximum total body dose of 40 mg subcutaneously (SC) every other week. In the OLE-FD phase, the subjects were treated with 20 mg of adalimumab SC every other week if their weight was less than 30 kg and with 40 mg of adalimumab SC every other week if their weight was 30 kg or greater. Subjects remained on stable doses of NSAIDs and or prednisone (≤0.2 mg/kg/day or 10 mg/day maximum).

Subjects demonstrating a Pediatric ACR 30 response at the end of OL-LI phase were randomized into the double blind (DB) phase of the study and received either adalimumab or placebo every other week for 32 weeks or until disease flare. Disease flare was defined as a worsening of ≥30% from baseline in ≥3 of 6 Pediatric ACR core criteria, ≥2 active joints, and improvement of >30% in no more than 1 of the 6 criteria. After 32 weeks or at the time of disease flare during the DB phase, subjects were treated in the open-label extension phase based on the BSA regimen (OLE-BSA), before converting to a fixed dose regimen based on body weight (OLE-FD phase).

Study JIA-I Clinical Response

At the end of the 16-week OL-LI phase, 94% of the subjects in the MTX stratum and 74% of the subjects in the non-MTX stratum were Pediatric ACR 30 responders. In the DB phase significantly fewer subjects who received adalimumab experienced disease flare compared to placebo, both without MTX (43% vs. 71%) and with MTX (37% vs. 65%). More subjects treated with adalimumab continued to show pediatric ACR 30/50/70 responses at Week 48 compared to subjects treated with placebo. Pediatric ACR responses were maintained for up to two years in the OLE phase in subjects who received adalimumab throughout the study.

Study JIA-II

Adalimumab was assessed in an open-label, multicenter study in 32 subjects who were 2 to <4 years of age or 4 years of age and older weighing <15 kg with moderately to severely active polyarticular JIA. Most subjects (97%) received at least 24 weeks of adalimumab treatment dosed 24 mg/m^2 up to a maximum of 20 mg every other week as a single SC injection up to a maximum of 120 weeks duration. During the study, most subjects used concomitant MTX, with fewer reporting use of corticosteroids or NSAIDs. The primary objective of the study was evaluation of safety [see Adverse Reactions (6.1)].

14.3 Clinical Studies in Psoriatic Arthritis

The safety and efficacy of adalimumab was assessed in two randomized, double-blind, placebo-controlled studies in 413 subjects with psoriatic arthritis (PsA). Upon completion of both studies, 383 subjects enrolled in an open-label extension study, in which 40 mg adalimumab was administered every other week.

Study PsA-I enrolled 313 adult subjects with moderately to severely active PsA (>3 swollen and >3 tender joints) who had an inadequate response to NSAID therapy in one of the following forms: (1) distal interphalangeal (DIP) involvement (N=23); (2) polyarticular arthritis (absence of rheumatoid nodules and presence of plaque psoriasis) (N=210); (3) arthritis mutilans (N=1); (4) asymmetric PsA (N=77); or (5) AS-like (N=2). Subjects on MTX therapy (158 of 313 subjects) at enrollment (stable dose of ≤30 mg/week for >1 month) could continue MTX at the same dose. Doses of adalimumab 40 mg or placebo every other week were administered during the 24-week double-blind period of the study.

Compared to placebo, treatment with adalimumab resulted in improvements in the measures of disease activity (see Tables 8 and 9). Among subjects with PsA who received adalimumab, the clinical responses were apparent in some subjects at the time of the first visit (two weeks) and were maintained up to 88 weeks in the ongoing open-label study. Similar responses were seen in subjects with each of the subtypes of psoriatic arthritis, although few subjects were enrolled with the arthritis mutilans and ankylosing spondylitis-like subtypes. Responses were similar in subjects who were or were not receiving concomitant MTX therapy at baseline.

Subjects with psoriatic involvement of at least three percent body surface area (BSA) were evaluated for Psoriatic Area and Severity Index (PASI) responses. At 24 weeks, the proportions of subjects achieving a 75% or 90% improvement in the PASI were 59% and 42% respectively, in the adalimumab group (N=69), compared to 1% and 0% respectively, in the placebo group (N=69) (p<0.001). PASI responses were apparent in some subjects at the time of the first visit (two weeks). Responses were similar in subjects who were or were not receiving concomitant MTX therapy at baseline.

Table 8. ACR Response in Study PsA-I (Percent of Subjects)
 | Placebo N=162 | Adalimumab* N=151
ACR20
Week 12 | 14% | 58%
Week 24 | 15% | 57%
ACR50
Week 12 | 4% | 36%
Week 24 | 6% | 39%
ACR70
Week 12 | 1% | 20%
Week 24 | 1% | 23%
*p<0.001 for all comparisons between adalimumab and placebo

Table 9. Components of Disease Activity in Study PsA-I
 | Placebo N=162 |  | Adalimumab* N=151
Parameter: median | Baseline | 24 weeks | Baseline | 24 weeks
Number of tender jointsa | 23.0 | 17.0 | 20.0 | 5.0
Number of swollen jointsb | 11.0 | 9.0 | 11.0 | 3.0
Physician global assessmentc | 53.0 | 49.0 | 55.0 | 16.0
Patient global assessmentc | 49.5 | 49.0 | 48.0 | 20.0
Painc | 49.0 | 49.0 | 54.0 | 20.0
Disability index (HAQ)d | 1.0 | 0.9 | 1.0 | 0.4
CRP (mg/dL)e | 0.8 | 0.7 | 0.8 | 0.2
*p<0.001 for adalimumab vs. placebo comparisons based on median changes
a Scale 0-78
b Scale 0-76
c Visual analog scale; 0=best, 100=worst
d Disability Index of the Health Assessment Questionnaire; 0=best, 3=worst; measures the patient's ability to perform the following: dress/groom, arise, eat, walk, reach, grip, maintain hygiene, and maintain daily activity.
e Normal range: 0-0.287 mg/dL

Similar results were seen in an additional, 12-week study in 100 subjects with moderate to severe psoriatic arthritis who had suboptimal response to DMARD therapy as manifested by ≥3 tender joints and ≥3 swollen joints at enrollment.

Radiographic Response

Radiographic changes were assessed in the PsA studies. Radiographs of hands, wrists, and feet were obtained at baseline and Week 24 during the double-blind period when subjects were on adalimumab or placebo and at Week 48 when all subjects were on open-label adalimumab. A modified Total Sharp Score (mTSS), which included distal interphalangeal joints (i.e., not identical to the TSS used for rheumatoid arthritis), was used by readers blinded to treatment group to assess the radiographs.

Adalimumab-treated subjects demonstrated greater inhibition of radiographic progression compared to placebo-treated subjects and this effect was maintained at 48 weeks (see Table 10).

Table 10. Change in Modified Total Sharp Score in Psoriatic Arthritis
 | Placebo N=141 | Adalimumab N=133
 | Week 24 | Week 24 | Week 48
Baseline mean | 22.1 | 23.4 | 23.4
Mean Change ± SD | 0.9 ± 3.1 | -0.1 ± 1.7 | -0.2 ± 4.9*
* <0.001 for the difference between adalimumab, Week 48 and Placebo, Week 24 (primary analysis)

Physical Function Response

In Study PsA-I, physical function and disability were assessed using the HAQ Disability Index (HAQ-DI) and the SF-36 Health Survey. Subjects treated with 40 mg of adalimumab every other week showed greater improvement from baseline in the HAQ-DI score (mean decreases of 47% and 49% at Weeks 12 and 24 respectively) in comparison to placebo (mean decreases of 1% and 3% at Weeks 12 and 24 respectively). At Weeks 12 and 24, subjects treated with adalimumab showed greater improvement from baseline in the SF-36 Physical Component Summary score compared to subjects treated with placebo, and no worsening in the SF-36 Mental Component Summary score. Improvement in physical function based on the HAQ-DI was maintained for up to 84 weeks through the open-label portion of the study.

14.4 Clinical Studies in Ankylosing Spondylitis

The safety and efficacy of adalimumab 40 mg every other week was assessed in 315 adult subjects in a randomized, 24 week double-blind, placebo-controlled study in subjects with active ankylosing spondylitis (AS) who had an inadequate response to glucocorticoids, NSAIDs, analgesics, methotrexate or sulfasalazine. Active AS was defined as subjects who fulfilled at least two of the following three criteria: (1) a Bath AS disease activity index (BASDAI) score ≥4 cm, (2) a visual analog score (VAS) for total back pain ≥40 mm, and (3) morning stiffness ≥1 hour. The blinded period was followed by an open-label period during which subjects received adalimumab 40 mg every other week subcutaneously for up to an additional 28 weeks.

Improvement in measures of disease activity was first observed at Week 2 and maintained through 24 weeks as shown in Figure 2 and Table 11.

Responses of subjects with total spinal ankylosis (n=11) were similar to those without total ankylosis.

Figure 2. ASAS 20 Response By Visit, Study AS-I

At 12 weeks, the ASAS 20/50/70 responses were achieved by 58%, 38%, and 23%, respectively, of subjects receiving adalimumab, compared to 21%, 10%, and 5% respectively, of subjects receiving placebo (p <0.001). Similar responses were seen at Week 24 and were sustained in subjects receiving open-label adalimumab for up to 52 weeks.

A greater proportion of subjects treated with adalimumab (22%) achieved a low level of disease activity at 24 weeks (defined as a value <20 [on a scale of 0 to 100 mm] in each of the four ASAS response parameters) compared to subjects treated with placebo (6%).

Table 11. Components of Ankylosing Spondylitis Disease Activity
 | Placebo N=107 |  | Adalimumab N=208
 | Baseline mean | Week 24 mean | Baseline mean | Week 24 mean
ASAS 20 Response Criteria*
Patient's Global Assessment of Disease Activitya* | 65 | 60 | 63 | 38
Total back pain* | 67 | 58 | 65 | 37
Inflammationb* | 6.7 | 5.6 | 6.7 | 3.6
BASFIc* | 56 | 51 | 52 | 34
BASDAId score* | 6.3 | 5.5 | 6.3 | 3.7
BASMIe score* | 4.2 | 4.1 | 3.8 | 3.3
Tragus to wall (cm) | 15.9 | 15.8 | 15.8 | 15.4
Lumbar flexion (cm) | 4.1 | 4.0 | 4.2 | 4.4
Cervical rotation (degrees) | 42.2 | 42.1 | 48.4 | 51.6
Lumbar side flexion (cm) | 8.9 | 9.0 | 9.7 | 11.7
Intermalleolar distance (cm) | 92.9 | 94.0 | 93.5 | 100.8
CRPf* | 2.2 | 2.0 | 1.8 | 0.6
a Percent of subjects with at least a 20% and 10-unit improvement measured on a Visual Analog Scale (VAS) with 0 = "none" and 100 = "severe"
b Mean of questions 5 and 6 of BASDAI (defined in 'd')
c Bath Ankylosing Spondylitis Functional Index
d Bath Ankylosing Spondylitis Disease Activity Index
e Bath Ankylosing Spondylitis Metrology Index
f C-Reactive Protein (mg/dL)
* statistically significant for comparisons between adalimumab and placebo at Week 24

A second randomized, multicenter, double-blind, placebo-controlled study of 82 subjects with ankylosing spondylitis showed similar results.

Subjects treated with adalimumab achieved improvement from baseline in the Ankylosing Spondylitis Quality of Life Questionnaire (ASQoL) score (-3.6 vs. -1.1) and in the Short Form Health Survey (SF-36) Physical Component Summary (PCS) score (7.4 vs. 1.9) compared to placebo-treated subjects at Week 24.

14.5 Clinical Studies in Adults with Crohn's Disease

The safety and efficacy of multiple doses of adalimumab were assessed in adult subjects with moderately to severely active Crohn's disease, CD, (Crohn's Disease Activity Index (CDAI) ≥220 and ≤450) in randomized, double-blind, placebo-controlled studies. Concomitant stable doses of aminosalicylates, corticosteroids, and/or immunomodulatory agents were permitted, and 79% of subjects continued to receive at least one of these medications.

Induction of clinical remission (defined as CDAI <150) was evaluated in two studies. In Study CD-I, 299 TNF-blocker naïve subjects were randomized to one of four treatment groups: the placebo group received placebo at Weeks 0 and 2, the 160/80 group received 160 mg adalimumab at Week 0 and 80 mg at Week 2, the 80/40 group received 80 mg at Week 0 and 40 mg at Week 2, and the 40/20 group received 40 mg at Week 0 and 20 mg at Week 2. Clinical results were assessed at Week 4.

In the second induction study, Study CD-II, 325 subjects who had lost response to, or were intolerant to, previous infliximab therapy were randomized to receive either 160 mg adalimumab at Week 0 and 80 mg at Week 2, or placebo at Weeks 0 and 2. Clinical results were assessed at Week 4.

Maintenance of clinical remission was evaluated in Study CD-III. In this study, 854 subjects with active disease received open-label adalimumab, 80 mg at week 0 and 40 mg at Week 2. Subjects were then randomized at Week 4 to 40 mg adalimumab every other week, 40 mg adalimumab every week, or placebo. The total study duration was 56 weeks. Subjects in clinical response (decrease in CDAI ≥70) at Week 4 were stratified and analyzed separately from those not in clinical response at Week 4.

Induction of Clinical Remission

A greater percentage of the subjects treated with 160/80 mg adalimumab achieved induction of clinical remission versus placebo at Week 4 regardless of whether the subjects were TNF blocker naïve (CD-I), or had lost response to or were intolerant to infliximab (CD-II) (see Table 12).

Table 12. Induction of Clinical Remission in Studies CD-I and CD-II (Percent of Subjects)
 | CD-I |  | CD-II
 | Placebo N=74 | Adalimumab 160/80 mg N=76 | Placebo N=166 | Adalimumab 160/80 mg N=159
Week 4
Clinical remission | 12% | 36%* | 7% | 21%*
Clinical response | 34% | 58%** | 34% | 52%**
Clinical remission is CDAI score <150; clinical response is decrease in CDAI of at least 70 points.
* p<0.001 for adalimumab vs. placebo pairwise comparison of proportions
** p<0.01 for adalimumab vs. placebo pairwise comparison of proportions

Maintenance of Clinical Remission

In Study CD-III at Week 4, 58% (499/854) of subjects were in clinical response and were assessed in the primary analysis. At Weeks 26 and 56, greater proportions of subjects who were in clinical response at Week 4 achieved clinical remission in the adalimumab 40 mg every other week maintenance group compared to subjects in the placebo maintenance group (see Table 13). The group that received adalimumab therapy every week did not demonstrate significantly higher remission rates compared to the group that received adalimumab every other week.

Table 13. Maintenance of Clinical Remission in CD-III (Percent of Subjects)
 | Placebo | 40 mg Adalimumab every other week
 | N=170 | N=172
Week 26
Clinical remission | 17% | 40%*
Clinical response | 28% | 54%*
Week 56
Clinical remission | 12% | 36%*
Clinical response | 18% | 43%*
Clinical remission is CDAI score <150; clinical response is decrease in CDAI of at least 70 points.
*p<0.001 for adalimumab vs. placebo pairwise comparisons of proportions

Of those in response at Week 4 who attained remission during the study, subjects in the adalimumab every other week group maintained remission for a longer time than subjects in the placebo maintenance group. Among subjects who were not in response by Week 12, therapy continued beyond 12 weeks did not result in significantly more responses.

14.6 Clinical Studies in Pediatric Subjects with Crohn's Disease

A randomized, double-blind, 52-week clinical study of 2 dose concentrations of adalimumab (Study PCD-I) was conducted in 192 pediatric subjects (6 to 17 years of age) with moderately to severely active Crohn's disease (defined as Pediatric Crohn's Disease Activity Index (PCDAI) score >30). Enrolled subjects had over the previous two-year period an inadequate response to corticosteroids or an immunomodulator (i.e., azathioprine, 6-mercaptopurine, or methotrexate). Subjects who had previously received a TNF blocker were allowed to enroll if they had previously had loss of response or intolerance to that TNF blocker.

Subjects received open-label induction therapy at a dose based on their body weight (≥40 kg and <40 kg). Subjects weighing ≥40 kg received 160 mg (at Week 0) and 80 mg (at Week 2). Subjects weighing <40 kg received 80 mg (at Week 0) and 40 mg (at Week 2). At Week 4, subjects within each body weight category (≥40 kg and <40 kg) were randomized 1:1 to one of two maintenance dose regimens (high dose and low dose). The high dose was 40 mg every other week for subjects weighing ≥40 kg and 20 mg every other week for subjects weighing <40 kg. The low dose was 20 mg every other week for subjects weighing ≥40 kg and 10 mg every other week for subjects weighing <40 kg.

Concomitant stable dosages of corticosteroids (prednisone dosage ≤40 mg/day or equivalent) and immunomodulators (azathioprine, 6-mercaptopurine, or methotrexate) were permitted throughout the study.

At Week 12, subjects who experienced a disease flare (increase in PCDAI of ≥15 from Week 4 and absolute PCDAI >30) or who were non-responders (did not achieve a decrease in the PCDAI of ≥15 from baseline for 2 consecutive visits at least 2 weeks apart) were allowed to dose-escalate (i.e., switch from blinded every other week dosing to blinded every week dosing); subjects who dose-escalated were considered treatment failures.

At baseline, 38% of subjects were receiving corticosteroids, and 62% of subjects were receiving an immunomodulator. Forty-four percent (44%) of subjects had previously lost response or were intolerant to a TNF blocker. The median baseline PCDAI score was 40.

Of the 192 subjects total, 188 subjects completed the 4 week induction period, 152 subjects completed 26 weeks of treatment, and 124 subjects completed 52 weeks of treatment. Fifty-one percent (51%) (48/95) of subjects in the low maintenance dose group dose-escalated, and 38% (35/93) of subjects in the high maintenance dose group dose-escalated.

At Week 4, 28% (52/188) of subjects were in clinical remission (defined as PCDAI ≤10).

The proportions of subjects in clinical remission (defined as PCDAI ≤10) and clinical response (defined as reduction in PCDAI of at least 15 points from baseline) were assessed at Weeks 26 and 52.

At both Weeks 26 and 52, the proportion of subjects in clinical remission and clinical response was numerically higher in the high dose group compared to the low dose group (Table 14). The recommended maintenance regimen is 20 mg every other week for subjects weighing <40 kg and 40 mg every other week for subjects weighing ≥40 kg. Every week dosing is not the recommended maintenance dosing regimen [see Dosage and Administration (2.4)].

Table 14. Clinical Remission and Clinical Response in Study PCD-I
 | Low Maintenance Dose† (20 or 10 mg every other week) N = 95 | High Maintenance Dose# (40 or 20 mg every other week) N = 93
Week 26
Clinical Remission‡ | 28% | 39%
Clinical Response§ | 48% | 59%
Week 52
Clinical Remission‡ | 23% | 33%
Clinical Response§ | 28% | 42%
† The low maintenance dose was 20 mg every other week for subjects weighing ≥40 kg and 10 mg every other week for subjects weighing <40 kg.
# The high maintenance dose was 40 mg every other week for subjects weighing ≥40 kg and 20 mg every other week for subjects weighing <40 kg.
‡ Clinical remission defined as PCDAI ≤10.
§ Clinical response defined as reduction in PCDAI of at least 15 points from baseline.

14.7 Clinical Studies in Adults with Ulcerative Colitis

The safety and efficacy of adalimumab were assessed in adult subjects with moderately to severely active ulcerative colitis (Mayo score 6 to 12 on a 12 point scale, with an endoscopy subscore of 2 to 3 on a scale of 0 to 3) despite concurrent or prior treatment with immunosuppressants such as corticosteroids, azathioprine, or 6-MP in two randomized, double-blind, placebo-controlled clinical studies (Studies UC-I and UC-II). Both studies enrolled TNF-blocker naïve subjects, but Study UC-II also allowed entry of subjects who lost response to or were intolerant to TNF-blockers. Forty percent (40%) of subjects enrolled in Study UC-II had previously used another TNF-blocker.

Concomitant stable doses of aminosalicylates and immunosuppressants were permitted. In Studies UC-I and II, subjects were receiving aminosalicylates (69%), corticosteroids (59%) and/or azathioprine or 6-MP (37%) at baseline. In both studies, 92% of subjects received at least one of these medications.

Induction of clinical remission (defined as Mayo score ≤2 with no individual subscores >1) at Week 8 was evaluated in both studies. Clinical remission at Week 52 and sustained clinical remission (defined as clinical remission at both Weeks 8 and 52) were evaluated in Study UC-II.

In Study UC-I, 390 TNF-blocker naïve subjects were randomized to one of three treatment groups for the primary efficacy analysis. The placebo group received placebo at Weeks 0, 2, 4 and 6. The 160/80 group received 160 mg adalimumab at Week 0 and 80 mg at Week 2, and the 80/40 group received 80 mg adalimumab at Week 0 and 40 mg at Week 2. After Week 2, subjects in both adalimumab treatment groups received 40 mg every other week.

In Study UC-II, 518 subjects were randomized to receive either adalimumab 160 mg at Week 0, 80 mg at Week 2, and 40 mg every other week starting at Week 4 through Week 50, or placebo starting at Week 0 and every other week through Week 50. Corticosteroid taper was permitted starting at Week 8.

In both Studies UC-I and UC-II, a greater percentage of the subjects treated with 160/80 mg of adalimumab compared to subjects treated with placebo achieved induction of clinical remission. In Study UC-II, a greater percentage of the subjects treated with 160/80 mg of adalimumab compared to subjects treated with placebo achieved sustained clinical remission (clinical remission at both Weeks 8 and 52) (Table 15).

Table 15. Induction of Clinical Remission in Studies UC-I and UC-II and Sustained Clinical Remission in Study UC-II (Percent of Subjects)
 | Study UC-I |  |  | Study UC-II
 | Placebo N=130 | Adalimumab 160/80 mg N=130 | Treatment Difference (95% CI) | Placebo N=246 | Adalimumab 160/80 mg N=248 | Treatment Difference (95% CI)
Induction of Clinical Remission (Clinical Remission at Week 8) | 9.2% | 18.5% | 9.3%* (0.9%, 17.6%) | 9.3% | 16.5% | 7.2%* (1.2%, 12.9%)
Sustained Clinical Remission (Clinical Remission at both Weeks 8 and 52) | N/A | N/A | N/A | 4.1% | 8.5% | 4.4%* (0.1%, 8.6%)
Clinical remission is defined as Mayo score ≤2 with no individual subscores >1.
CI=Confidence interval
* p<0.05 for adalimumab vs. placebo pairwise comparison of proportions

In Study UC-I, there was no statistically significant difference in clinical remission observed between the adalimumab 80/40 mg group and the placebo group at Week 8.

In Study UC-II, 17.3% (43/248) in the adalimumab group were in clinical remission at Week 52 compared to 8.5% (21/246) in the placebo group (treatment difference: 8.8%; 95% confidence interval (CI): [2.8%, 14.5%]; p<0.05).

In the subgroup of subjects in Study UC-II with prior TNF-blocker use, the treatment difference for induction of clinical remission appeared to be lower than that seen in the whole study population, and the treatment differences for sustained clinical remission and clinical remission at Week 52 appeared to be similar to those seen in the whole study population. The subgroup of subjects with prior TNF-blocker use achieved induction of clinical remission at 9% (9/98) in the adalimumab group versus 7% (7/101) in the placebo group, and sustained clinical remission at 5% (5/98) in the adalimumab group versus 1% (1/101) in the placebo group. In the subgroup of subjects with prior TNF-blocker use, 10% (10/98) were in clinical remission at Week 52 in the adalimumab group versus 3% (3/101) in the placebo group.

14.8 Clinical Studies in Plaque Psoriasis

The safety and efficacy of adalimumab were assessed in randomized, double-blind, placebo-controlled studies in 1696 adult subjects with moderate to severe chronic plaque psoriasis (Ps) who were candidates for systemic therapy or phototherapy.

Study Ps-I evaluated 1212 subjects with chronic Ps with ≥10% body surface area (BSA) involvement, Physician's Global Assessment (PGA) of at least moderate disease severity, and Psoriasis Area and Severity Index (PASI) ≥12 within three treatment periods. In period A, subjects received placebo or adalimumab at an initial dose of 80 mg at Week 0 followed by a dose of 40 mg every other week starting at Week 1. After 16 weeks of therapy, subjects who achieved at least a PASI 75 response at Week 16, defined as a PASI score improvement of at least 75% relative to baseline, entered period B and received open-label 40 mg adalimumab every other week. After 17 weeks of open label therapy, subjects who maintained at least a PASI 75 response at Week 33 and were originally randomized to active therapy in period A were re-randomized in period C to receive 40 mg adalimumab every other week or placebo for an additional 19 weeks. Across all treatment groups the mean baseline PASI score was 19 and the baseline Physician's Global Assessment score ranged from "moderate" (53%) to "severe" (41%) to "very severe" (6%).

Study Ps-II evaluated 99 subjects randomized to adalimumab and 48 subjects randomized to placebo with chronic plaque psoriasis with ≥10% BSA involvement and PASI ≥12. Subjects received placebo, or an initial dose of 80 mg adalimumab at Week 0 followed by 40 mg every other week starting at Week 1 for 16 weeks. Across all treatment groups the mean baseline PASI score was 21 and the baseline PGA score ranged from "moderate" (41%) to "severe" (51%) to "very severe" (8%).

Studies Ps-I and II evaluated the proportion of subjects who achieved "clear" or "minimal" disease on the 6-point PGA scale and the proportion of subjects who achieved a reduction in PASI score of at least 75% (PASI 75) from baseline at Week 16 (see Table 16 and 17).

Additionally, Study Ps-I evaluated the proportion of subjects who maintained a PGA of "clear" or "minimal" disease or a PASI 75 response after Week 33 and on or before Week 52.

Table 16. Efficacy Results at 16 Weeks in Study Ps-I Number of Subjects (%)
 | Adalimumab 40 mg every other week | Placebo
 | N=814 | N=398
PGA: Clear or minimal* | 506 (62%) | 17 (4%)
PASI 75 | 578 (71%) | 26 (7%)
* Clear = no plaque elevation, no scale, plus or minus hyperpigmentation or diffuse pink or red coloration
Minimal = possible but difficult to ascertain whether there is slight elevation of plaque above normal skin, plus or minus surface dryness with some white coloration, plus or minus up to red coloration

Table 17. Efficacy Results at 16 Weeks in Study Ps-II Number of Subjects (%)
 | Adalimumab 40 mg every other week | Placebo
 | N=99 | N=48
PGA: Clear or minimal* | 70 (71%) | 5 (10%)
PASI 75 | 77 (78%) | 9 (19%)
* Clear = no plaque elevation, no scale, plus or minus hyperpigmentation or diffuse pink or red coloration
Minimal = possible but difficult to ascertain whether there is slight elevation of plaque above normal skin, plus or minus surface dryness with some white coloration, plus or minus up to red coloration

Additionally, in Study Ps-I, subjects on adalimumab who maintained a PASI 75 were re-randomized to adalimumab (N=250) or placebo (N=240) at Week 33. After 52 weeks of treatment with adalimumab, more subjects on adalimumab maintained efficacy when compared to subjects who were re-randomized to placebo based on maintenance of PGA of "clear" or "minimal" disease (68% vs. 28%) or a PASI 75 (79% vs. 43%).

A total of 347 stable responders participated in a withdrawal and retreatment evaluation in an open-label extension study. Median time to relapse (decline to PGA "moderate" or worse) was approximately 5 months. During the withdrawal period, no subject experienced transformation to either pustular or erythrodermic psoriasis. A total of 178 subjects who relapsed re-initiated treatment with 80 mg of adalimumab, then 40 mg every other week beginning at week 1. At week 16, 69% (123/178) of subjects had a response of PGA "clear" or "minimal".

A randomized, double-blind study (Study Ps-III) compared the efficacy and safety of adalimumab versus placebo in 217 adult subjects. Subjects in the study had to have chronic plaque psoriasis of at least moderate severity on the PGA scale, fingernail involvement of at least moderate severity on a 5-point Physician's Global Assessment of Fingernail Psoriasis (PGA-F) scale, a Modified Nail Psoriasis Severity Index (mNAPSI) score for the target-fingernail of ≥8, and either a BSA involvement of at least 10% or a BSA involvement of at least 5% with a total mNAPSI score for all fingernails of ≥20. Subjects received an initial dose of 80 mg adalimumab followed by 40 mg every other week (starting one week after the initial dose) or placebo for 26 weeks followed by open-label adalimumab treatment for an additional 26 weeks. This study evaluated the proportion of subjects who achieved "clear" or "minimal" assessment with at least a 2-grade improvement on the PGA-F scale and the proportion of subjects who achieved at least a 75% improvement from baseline in the mNAPSI score (mNAPSI 75) at Week 26.

At Week 26, a higher proportion of subjects in the adalimumab group than in the placebo group achieved the PGA-F endpoint. Furthermore, a higher proportion of subjects in the adalimumab group than in the placebo group achieved mNAPSI 75 at Week 26 (see Table 18).

Table 18. Efficacy Results at 26 Weeks
Endpoint | Adalimumab 40 mg every other week* N=109 | Placebo N=108
PGA-F: ≥2-grade improvement and clear or minimal | 49% | 7%
mNAPSI 75 | 47% | 3%
*Subjects received 80 mg of adalimumab at Week 0, followed by 40 mg every other week starting at Week 1.

Nail pain was also evaluated and improvement in nail pain was observed in Study Ps-III.

14.9 Clinical Studies in Hidradenitis Suppurativa

Two randomized, double-blind, placebo-controlled studies (Studies HS-I and II) evaluated the safety and efficacy of adalimumab in a total of 633 adult subjects with moderate to severe hidradenitis suppurativa (HS) with Hurley Stage II or III disease and with at least 3 abscesses or inflammatory nodules. In both studies, subjects received placebo or adalimumab at an initial dose of 160 mg at Week 0, 80 mg at Week 2, and 40 mg every week starting at Week 4 and continued through Week 11. Subjects used topical antiseptic wash daily. Concomitant oral antibiotic use was allowed in Study HS-II.

Both studies evaluated Hidradenitis Suppurativa Clinical Response (HiSCR) at Week 12. HiSCR was defined as at least a 50% reduction in total abscess and inflammatory nodule count with no increase in abscess count and no increase in draining fistula count relative to baseline (see Table 19). Reduction in HS-related skin pain was assessed using a Numeric Rating Scale in subjects who entered the study with an initial baseline score of 3 or greater on a 11-point scale.

In both studies, a higher proportion of adalimumab- than placebo-treated subjects achieved HiSCR (see Table 19).

Table 19. Efficacy Results at 12 Weeks in Subjects with Moderate to Severe Hidradenitis Suppurativa
 | HS Study I |  | HS Study II*
 | Placebo | Adalimumab 40 mg Weekly | Placebo | Adalimumab 40 mg Weekly
Hidradenitis Suppurativa Clinical Response (HiSCR) | N = 154 40 (26%) | N = 153 64 (42%) | N=163 45 (28%) | N=163 96 (59%)
*19.3% of subjects in Study HS-II continued baseline oral antibiotic therapy during the study.

In both studies, from Week 12 to Week 35 (Period B), subjects who had received adalimumab were re-randomized to 1 of 3 treatment groups (adalimumab 40 mg every week, adalimumab 40 mg every other week, or placebo). Subjects who had been randomized to placebo were assigned to receive adalimumab 40 mg every week (Study HS-I) or placebo (Study HS-II).

During Period B, flare of HS, defined as ≥25% increase from baseline in abscesses and inflammatory nodule counts and with a minimum of 2 additional lesions, was documented in 22 (22%) of the 100 subjects who were withdrawn from adalimumab treatment following the primary efficacy timepoint in two studies.

14.10 Clinical Studies in Adults with Uveitis

The safety and efficacy of adalimumab were assessed in adult subjects with non-infectious intermediate, posterior and panuveitis excluding subjects with isolated anterior uveitis, in two randomized, double-masked, placebo-controlled studies (UV I and II). Subjects received placebo or adalimumab at an initial dose of 80 mg followed by 40 mg every other week starting one week after the initial dose. The primary efficacy endpoint in both studies was 'time to treatment failure'.

Treatment failure was a multi-component outcome defined as the development of new inflammatory chorioretinal and/or inflammatory retinal vascular lesions, an increase in anterior chamber (AC) cell grade or vitreous haze (VH) grade or a decrease in best corrected visual acuity (BCVA).

Study UV I evaluated 217 subjects with active uveitis while being treated with corticosteroids (oral prednisone at a dose of 10 to 60 mg/day). All subjects received a standardized dose of prednisone 60 mg/day at study entry followed by a mandatory taper schedule, with complete corticosteroid discontinuation by Week 15.

Study UV II evaluated 226 subjects with inactive uveitis while being treated with corticosteroids (oral prednisone 10 to 35 mg/day) at baseline to control their disease. Subjects subsequently underwent a mandatory taper schedule, with complete corticosteroid discontinuation by Week 19.

Clinical Response

Results from both studies demonstrated statistically significant reduction of the risk of treatment failure in subjects treated with adalimumab versus subjects receiving placebo. In both studies, all components of the primary endpoint contributed cumulatively to the overall difference between adalimumab and placebo groups (Table 20).

Table 20. Time to Treatment Failure in Studies UV I and UV II
 | UV I |  |  | UV II
 | Placebo (N = 107) | Adalimumab (N = 110) | HR [95% CI]a | Placebo (N = 111) | Adalimumab (N = 115) | HR [95% CI]a
Failureb n (%) | 84 (78.5) | 60 (54.5) | 0.50 [0.36, 0.70] | 61 (55.0) | 45 (39.1) | 0.57 [0.39, 0.84]
Median Time to Failure (Months) [95% CI] | 3.0 [2.7, 3.7] | 5.6 [3.9, 9.2] | N/A | 8.3 [4.8, 12.0] | NEc | N/A
a HR of adalimumab versus placebo from proportional hazards regression with treatment as factor.
b Treatment failure at or after Week 6 in Study UV I, or at or after Week 2 in Study UV II, was counted as event. Subjects who discontinued the study were censored at the time of dropping out.
c NE = not estimable. Fewer than half of at-risk subjects had an event.

Figure 3. Kaplan-Meier Curves Summarizing Time to Treatment Failure on or after Week 6 (Study UV I) or Week 2 (Study UV II)

Study UV I

Study UV II

Note: P# = Placebo (Number of Events/Number at Risk); A# = Adalimumab (Number of Events/Number at Risk).

14.11 Clinical Studies in Pediatric Subjects with Uveitis

The safety and efficacy of adalimumab were assessed in a randomized, double-masked, placebo-controlled study of 90 pediatric subjects from 2 to < 18 years of age with active JIA-associated non-infectious uveitis (PUV-I). Subjects received either placebo or 20 mg adalimumab (if < 30 kg) or 40 mg adalimumab (if ≥ 30 kg) every other week in combination with a dose of methotrexate. Concomitant dosages of corticosteroids were permitted at study entry followed by a mandatory reduction in topical corticosteroids within 3 months.

The primary endpoint was 'time to treatment failure'. The criteria determining treatment failure were worsening or sustained non-improvement in ocular inflammation, or worsening of ocular co-morbidities.

Clinical Response

Adalimumab significantly decreased the risk of treatment failure by 75% relative to placebo (HR = 0.25 [95% CI: 0.12, 0.49]) (Table 21).

Table 21. Analysis Results of Time to Treatment Failure (Study PUV-I)
 | Placebo (N = 30) | Adalimumab (N = 60) | HR (95% CI)a
Failure (n [%]) | 18 (60%) | 16 (26.7%) | 0.25 (0.12, 0.49)
Median Time to Failure (Weeks) (95% CI)b | 24.1 (12.4, 81.0) | NEc
aHR of adalimumab versus placebo from proportional hazards regression with treatment as factor.
bEstimated based on Kaplan-Meier curve.
cNE = not estimable. Fewer than half of at-risk subjects had an event.

Figure 4. Kaplan-Meier Curves Summarizing Time to Treatment Failure (Study PUV-I)

Study PUV-I
Note: P = Placebo (Number at Risk); A = Adalimumab (Number at Risk)

15 REFERENCES

1. National Cancer Institute. Surveillance, Epidemiology, and End Results Database (SEER) Program. SEER Incidence Crude Rates, 17 Registries, 2000-2007.

16 HOW SUPPLIED/STORAGE AND HANDLING

Adalimumab-adbm injection is supplied as a sterile, preservative-free, clear to slightly opalescent and colorless to slightly yellow solution for subcutaneous administration. The following packaging configurations are available.

Adalimumab-adbm Pen Prefilled Pen | Contents | Number of Units/Carton | NDC number
40 mg/0.8 mL | 2 dose trays* and 2 alcohol preps | 2 | 0597-0545-22
40 mg/0.4 mL | 2 dose trays** and 2 alcohol preps | 2 | 0597-0575-50
*Each dose tray consists of a single-dose pen, containing a 1 mL prefilled glass syringe with a fixed ½ inch needle, providing 40 mg/0.8 mL of Adalimumab-adbm. The needle cap contains natural rubber latex.
**Each dose tray consists of a single-dose pen, containing a 1 mL prefilled glass syringe with a fixed ½ inch needle, providing 40 mg/0.4 mL of Adalimumab-adbm. The needle cap contains natural rubber latex.

Adalimumab-adbm Prefilled Syringe | Contents* | Number of Units/Carton | NDC number
10 mg/0.2 mL | 2 dose trays and 2 alcohol preps | 2 | 0597-0585-89
20 mg/0.4 mL | 2 dose trays and 2 alcohol preps | 2 | 0597-0555-80
40 mg/0.4 mL | 2 dose trays and 2 alcohol preps | 2 | 0597-0565-20
40 mg/0.8 mL | 2 dose trays and 2 alcohol preps | 2 | 0597-0595-20
*Each dose tray consists of a single-dose, 1 mL prefilled glass syringe with a fixed, ½ inch needle. The needle cap contains natural rubber latex.

Storage and Stability

Do not use beyond the expiration date on the container. Adalimumab-adbm must be refrigerated at 36°F to 46°F (2°C to 8°C). DO NOT FREEZE. Do not use if frozen even if it has been thawed.

Store in original carton until time of administration to protect from light.

If needed, for example when traveling, Adalimumab-adbm may be stored at room temperature up to a maximum of 77°F (25°C) for a period of up to 14 days, with protection from light. Adalimumab-adbm should be discarded if not used within the 14-day period. Record the date when Adalimumab-adbm is first removed from the refrigerator in the spaces provided on the carton and dose tray.

Do not store Adalimumab-adbm in extreme heat or cold.

17 PATIENT COUNSELING INFORMATION

Advise the patient or caregiver to read the FDA-approved patient labeling (Medication Guide and Instructions for Use).

Infections

Inform patients that Adalimumab-adbm may lower the ability of their immune system to fight infections. Instruct patients of the importance of contacting their doctor if they develop any symptoms of infection, including tuberculosis, invasive fungal infections, and reactivation of hepatitis B virus infections [see Warnings and Precautions (5.1, 5.2, 5.4)].

Malignancies

Counsel patients about the risk of malignancies while receiving Adalimumab-adbm [see Warnings and Precautions (5.2)].

Hypersensitivity Reactions

Advise patients to seek immediate medical attention if they experience any symptoms of severe hypersensitivity reactions. Advise latex-sensitive patients that the needle cap of the Adalimumab-adbm Pen and prefilled syringe contains natural rubber latex [see Warnings and Precautions (5.3), How Supplied/Storage and Handling (16)].

Other Medical Conditions

Advise patients to report any signs of new or worsening medical conditions such as congestive heart failure, neurological disease, autoimmune disorders, or cytopenias. Advise patients to report any symptoms suggestive of a cytopenia such as bruising, bleeding, or persistent fever [see Warnings and Precautions (5.5, 5.6, 5.8, 5.9)].

Instructions on Injection Technique

Inform patients that the first injection is to be performed under the supervision of a qualified health care professional. If a patient or caregiver is to administer Adalimumab-adbm, instruct them in injection techniques and assess their ability to inject subcutaneously to ensure the proper administration of Adalimumab-adbm [see Instructions for Use].

For patients who will use the Adalimumab-adbm Pen, tell them that they:

- Will hear a 'click' when the injection button is pressed. The click indicates the start of the injection.
- Must keep holding the Adalimumab-adbm Pen against their squeezed, raised skin until all of the medicine is injected. This can take up to 10 seconds.
- Confirm entire dose was delivered by making sure plunger (seen in window) reached the bottom of the pen.

Instruct patients to dispose of their used needles and syringes or used pens in an FDA-cleared sharps disposal container immediately after use. Instruct patients not to dispose of loose needles and syringes or pens in their household trash. Instruct patients that if they do not have an FDA-cleared sharps disposal container, they may use a household container that is made of a heavy-duty plastic, can be closed with a tight-fitting and puncture-resistant lid without sharps being able to come out, upright and stable during use, leak-resistant, and properly labeled to warn of hazardous waste inside the container.

Instruct patients that when their sharps disposal container is almost full, they will need to follow their community guidelines for the correct way to dispose of their sharps disposal container. Instruct patients that there may be state or local laws regarding disposal of used needles and syringes. Refer patients to the FDA's website at http://www.fda.gov/safesharpsdisposal for more information about safe sharps disposal, and for specific information about sharps disposal in the state that they live in.

Instruct patients not to dispose of their used sharps disposal container in their household trash unless their community guidelines permit this. Instruct patients not to recycle their used sharps disposal container.

Address medical inquiries to: (800) 542-6257.

Manufactured by:
Boehringer Ingelheim Pharmaceuticals, Inc.
Ridgefield, CT 06877 USA
US License Number 2006

CYLTEZO® is a registered trademark of and is used under license from Boehringer Ingelheim International GmbH.

HUMIRA® and other trademarks referenced are owned by third parties not affiliated with Boehringer Ingelheim Pharmaceuticals, Inc.

Copyright © 2025 Boehringer Ingelheim International GmbH
ALL RIGHTS RESERVED

COL12314DJ092025
SPL12317D

MEDICATION GUIDE
Adalimumab-adbm (ada-LIM-u-mab adbm)
injection, for subcutaneous use
This product is CYLTEZO® (adalimumab-adbm).

Read the Medication Guide that comes with Adalimumab-adbm before you start taking it and each time you get a refill. There may be new information. This Medication Guide does not take the place of talking with your doctor about your medical condition or treatment.

What is the most important information I should know about Adalimumab-adbm?

Adalimumab-adbm is a medicine that affects your immune system. Adalimumab-adbm can lower the ability of your immune system to fight infections. Serious infections have happened in people taking adalimumab products. These serious infections include tuberculosis (TB) and infections caused by viruses, fungi or bacteria that have spread throughout the body. Some people have died from these infections.

- Your doctor should test you for TB before starting Adalimumab-adbm.
- Your doctor should check you closely for signs and symptoms of TB during treatment with Adalimumab-adbm.

You should not start taking Adalimumab-adbm if you have any kind of infection unless your doctor says it is okay.

Before starting Adalimumab-adbm, tell your doctor if you:

- think you have an infection or have symptoms of an infection such as:

- fever, sweats, or chills
- muscle aches
- cough
- shortness of breath
- blood in phlegm
- warm, red or painful skin or sores on your body

- diarrhea or stomach pain
- burning when you urinate or urinate more often than normal
- feel very tired
- weight loss

- are being treated for an infection.
- get a lot of infections or have infections that keep coming back.
- have diabetes.
- have TB, or have been in close contact with someone with TB.
- were born in, lived in, or traveled to countries where there is more risk for getting TB. Ask your doctor if you are not sure.
- live or have lived in certain parts of the country (such as the Ohio and Mississippi River valleys) where there is an increased risk for getting certain kinds of fungal infections (histoplasmosis, coccidioidomycosis, or blastomycosis). These infections may happen or become more severe if you use Adalimumab-adbm. Ask your doctor if you do not know if you have lived in an area where these infections are common.
- have or have had hepatitis B.
- use the medicine ORENCIA (abatacept), KINERET (anakinra), RITUXAN (rituximab), IMURAN (azathioprine), or PURINETHOL (6-mercaptopurine, 6-MP).
- are scheduled to have major surgery.

After starting Adalimumab-adbm, call your doctor right away if you have an infection, or any sign of an infection.

Adalimumab-adbm can make you more likely to get infections or make any infection that you may have worse.

Cancer

- For children and adults taking Tumor Necrosis Factor (TNF)-blockers, including Adalimumab-adbm, the chances of getting cancer may increase.
- There have been cases of unusual cancers in children, teenagers, and young adults using TNF-blockers.
- People with rheumatoid arthritis (RA), especially more serious RA, may have a higher chance for getting a kind of cancer called lymphoma.
- If you use TNF blockers including Adalimumab-adbm your chance of getting two types of skin cancer may increase (basal cell cancer and squamous cell cancer of the skin). These types of cancer are generally not life-threatening if treated. Tell your doctor if you have a bump or open sore that does not heal.
- Some people receiving TNF blockers including Adalimumab-adbm developed a rare type of cancer called hepatosplenic T-cell lymphoma. This type of cancer often results in death. Most of these people were male teenagers or young men. Also, most people were being treated for Crohn's disease or ulcerative colitis with another medicine called IMURAN (azathioprine) or PURINETHOL (6-mercaptopurine, 6-MP).

What is Adalimumab-adbm?

Adalimumab-adbm is a medicine called a Tumor Necrosis Factor (TNF) blocker. Adalimumab-adbm is used:

- To reduce the signs and symptoms of:
  - moderate to severe RA in adults. Adalimumab-adbm can be used alone, with methotrexate, or with certain other medicines.
  - moderate to severe polyarticular juvenile idiopathic arthritis (JIA) in children 2 years and older. Adalimumab-adbm can be used alone or with methotrexate.
  - psoriatic arthritis (PsA) in adults. Adalimumab-adbm can be used alone or with certain other medicines.
  - ankylosing spondylitis (AS) in adults.
  - moderate to severe hidradenitis suppurativa (HS) in people 12 years and older.
- To treat moderate to severe Crohn's disease (CD) in adults and children 6 years of age and older.
- To treat moderate to severe ulcerative colitis (UC) in adults. It is not known if adalimumab products are effective in people who stopped responding to or could not tolerate TNF-blocker medicines.
- To treat moderate to severe chronic (lasting a long time) plaque psoriasis (Ps) in adults who have the condition in many areas of their body and who may benefit from taking injections or pills (systemic therapy) or phototherapy (treatment using ultraviolet light alone or with pills).
- To treat non-infectious intermediate, posterior, and panuveitis in adults and children 2 years of age and older.

What should I tell my doctor before taking Adalimumab-adbm?

Adalimumab-adbm may not be right for you. Before starting Adalimumab-adbm, tell your doctor about all of your medical conditions, including if you:

- have an infection. See "What is the most important information I should know about Adalimumab-adbm?"
- have or have had cancer.
- have any numbness or tingling or have a disease that affects your nervous system such as multiple sclerosis or Guillain-Barré syndrome.
- have or had heart failure.
- have recently received or are scheduled to receive a vaccine. You may receive vaccines, except for live vaccines while using Adalimumab-adbm. Children should be brought up to date with all vaccines before starting Adalimumab-adbm.
- are allergic to rubber or latex. The needle cap on the Adalimumab-adbm Pen and prefilled syringe contains dry natural rubber or latex. Tell your doctor if you have any allergies to rubber or latex.
- are allergic to Adalimumab-adbm or to any of its ingredients. See the end of this Medication Guide for a list of ingredients in Adalimumab-adbm.
- are pregnant or plan to become pregnant, breastfeeding or plan to breastfeed. You and your doctor should decide if you should take Adalimumab-adbm while you are pregnant or breastfeeding.
- have a baby and you were using Adalimumab-adbm during your pregnancy. Tell your baby's doctor before your baby receives any vaccines.

Tell your doctor about all the medicines you take, including prescription and over-the-counter medicines, vitamins, and herbal supplements.

Especially tell your doctor if you use:

- ORENCIA (abatacept), KINERET (anakinra), REMICADE (infliximab), ENBREL (etanercept), CIMZIA (certolizumab pegol) or SIMPONI (golimumab), because you should not use Adalimumab-adbm while you are also using one of these medicines.
- RITUXAN (rituximab). Your doctor may not want to give you Adalimumab-adbm if you have received RITUXAN (rituximab) recently.
- IMURAN (azathioprine) or PURINETHOL (6-mercaptopurine, 6-MP).

Keep a list of your medicines with you to show your doctor and pharmacist each time you get a new medicine.

How should I take Adalimumab-adbm?

- Adalimumab-adbm is given by an injection under the skin. Your doctor will tell you how often to take an injection of Adalimumab-adbm. This is based on your condition to be treated. Do not inject Adalimumab-adbm more often than you were prescribed.
- See the Instructions for Use inside the carton for complete instructions for the right way to prepare and inject Adalimumab-adbm.
- Make sure you have been shown how to inject Adalimumab-adbm before you do it yourself. You can call your doctor or 1-800-542-6257 if you have any questions about giving yourself an injection. Someone you know can also help you with your injection after they have been shown how to prepare and inject Adalimumab-adbm.
- Do not try to inject Adalimumab-adbm yourself until you have been shown the right way to give the injections. If your doctor decides that you or a caregiver may be able to give your injections of Adalimumab-adbm at home, you should receive training on the right way to prepare and inject Adalimumab-adbm.
- Do not miss any doses of Adalimumab-adbm unless your doctor says it is okay. If you forget to take Adalimumab-adbm, inject a dose as soon as you remember. Then, take your next dose at your regular scheduled time. This will put you back on schedule. In case you are not sure when to inject Adalimumab-adbm, call your doctor or pharmacist.
- If you take more Adalimumab-adbm than you were told to take, call your doctor.

What are the possible side effects of Adalimumab-adbm?

Adalimumab-adbm can cause serious side effects, including:

See "What is the most important information I should know about Adalimumab-adbm?"

- Serious Infections. Your doctor will examine you for TB and perform a test to see if you have TB. If your doctor feels that you are at risk for TB, you may be treated with medicine for TB before you begin treatment with Adalimumab-adbm and during treatment with Adalimumab-adbm. Even if your TB test is negative your doctor should carefully monitor you for TB infections while you are taking Adalimumab-adbm. People who had a negative TB skin test before receiving adalimumab products have developed active TB. Tell your doctor if you have any of the following symptoms while taking or after taking Adalimumab-adbm:

- cough that does not go away
- low grade fever

- weight loss
- loss of body fat and muscle (wasting)

- Hepatitis B infection in people who carry the virus in their blood. If you are a carrier of the hepatitis B virus (a virus that affects the liver), the virus can become active while you use Adalimumab-adbm. Your doctor should do blood tests before you start treatment, while you are using Adalimumab-adbm, and for several months after you stop treatment with Adalimumab-adbm. Tell your doctor if you have any of the following symptoms of a possible hepatitis B infection:

- muscle aches
- feel very tired
- dark urine
- skin or eyes look yellow
- little or no appetite
- vomiting

- clay-colored bowel movements
- fever
- chills
- stomach discomfort
- skin rash

- Allergic reactions. Allergic reactions can happen in people who use Adalimumab-adbm. Call your doctor or get medical help right away if you have any of these symptoms of a serious allergic reaction:

- hives
- trouble breathing

- swelling of your face, eyes, lips or mouth

- Nervous system problems. Signs and symptoms of a nervous system problem include: numbness or tingling, problems with your vision, weakness in your arms or legs, and dizziness.
- Blood problems. Your body may not make enough of the blood cells that help fight infections or help to stop bleeding. Symptoms include a fever that does not go away, bruising or bleeding very easily, or looking very pale.
- New heart failure or worsening of heart failure you already have. Call your doctor right away if you get new worsening symptoms of heart failure while taking Adalimumab-adbm, including:

- shortness of breath
- sudden weight gain

- swelling of your ankles or feet

- Immune reactions including a lupus-like syndrome. Symptoms include chest discomfort or pain that does not go away, shortness of breath, joint pain, or a rash on your cheeks or arms that gets worse in the sun. Symptoms may improve when you stop Adalimumab-adbm.
- Liver problems. Liver problems can happen in people who use TNF-blocker medicines. These problems can lead to liver failure and death. Call your doctor right away if you have any of these symptoms:

- feel very tired
- poor appetite or vomiting

- skin or eyes look yellow
- pain on the right side of your stomach (abdomen)

- Psoriasis. Some people using adalimumab products had new psoriasis or worsening of psoriasis they already had. Tell your doctor if you develop red scaly patches or raised bumps that are filled with pus. Your doctor may decide to stop your treatment with Adalimumab-adbm.

Call your doctor or get medical care right away if you develop any of the above symptoms. Your treatment with Adalimumab-adbm may be stopped.

The most common side effects of Adalimumab-adbm include:

- injection site reactions: redness, rash, swelling, itching, or bruising. These symptoms usually will go away within a few days. Call your doctor right away if you have pain, redness or swelling around the injection site that does not go away within a few days or gets worse.
- upper respiratory infections (including sinus infections).
- headaches.
- rash.

These are not all the possible side effects with Adalimumab-adbm. Tell your doctor if you have any side effect that bothers you or that does not go away. Ask your doctor or pharmacist for more information.

Call your doctor for medical advice about side effects. You may report side effects to FDA at 1-800-FDA-1088.

How should I store Adalimumab-adbm?

- Store Adalimumab-adbm in the refrigerator at 36°F to 46°F (2°C to 8°C). Store Adalimumab-adbm in the original carton until use to protect it from light.
- Do not freeze Adalimumab-adbm. Do not use Adalimumab-adbm if frozen, even if it has been thawed.
- Refrigerated Adalimumab-adbm may be used until the expiration date printed on the Adalimumab-adbm carton, dose tray, pen, or prefilled syringe. Do not use Adalimumab-adbm after the expiration date.
- If needed, for example when you are traveling, you may also store Adalimumab-adbm at room temperature up to 77°F (25°C) for up to 14 days. Store Adalimumab-adbm in the original carton until use to protect it from light.
- Throw away Adalimumab-adbm if it has been kept at room temperature and not been used within 14 days.
- Record the date you first remove Adalimumab-adbm from the refrigerator in the spaces provided on the carton and dose tray.
- Do not store Adalimumab-adbm in extreme heat or cold.
- Do not use a pen or prefilled syringe if the liquid is milky, discolored, or has flakes or particles in it.
- Do not drop or crush Adalimumab-adbm. The prefilled syringe is glass.

Keep Adalimumab-adbm, injection supplies, and all other medicines out of the reach of children.

General information about the safe and effective use of Adalimumab-adbm.

Medicines are sometimes prescribed for purposes other than those listed in a Medication Guide. Do not use Adalimumab-adbm for a condition for which it was not prescribed. Do not give Adalimumab-adbm to other people, even if they have the same condition. It may harm them.

This Medication Guide summarizes the most important information about Adalimumab-adbm. If you would like more information, talk with your doctor. You can ask your pharmacist or doctor for information about Adalimumab-adbm that is written for health professionals. For more information, call 1-800-542-6257.

What are the ingredients in Adalimumab-adbm?

Active ingredient: adalimumab-adbm

Adalimumab-adbm Pen 40 mg/0.8 mL, Adalimumab-adbm 40 mg/0.8 mL prefilled syringe, Adalimumab-adbm Pen 40 mg/0.4 mL, Adalimumab-adbm 40 mg/0.4 mL prefilled syringe, Adalimumab-adbm 20 mg/0.4 mL prefilled syringe, and Adalimumab-adbm 10 mg/0.2 mL prefilled syringe

Inactive ingredients: glacial acetic acid, polysorbate 80, sodium acetate trihydrate, trehalose dihydrate, and Water for Injection.

Manufactured by: Boehringer Ingelheim Pharmaceuticals, Inc., Ridgefield, CT 06877 USA
US License Number 2006

CYLTEZO® is a registered trademark of and is used under license from Boehringer Ingelheim International GmbH.
Other trademarks referenced are owned by third parties not affiliated with Boehringer Ingelheim Pharmaceuticals, Inc.

For more information about Adalimumab-adbm, scan the code or call 1-800-542-6257.

Copyright © 2025 Boehringer Ingelheim International GmbH. ALL RIGHTS RESERVED
COL12315DJ092025

This Medication Guide has been approved by the U.S. Food and Drug Administration.

Revised: 10/2025

INSTRUCTIONS FOR USE Adalimumab-adbm (ada-LIM-u-mab adbm) Pen injection, for subcutaneous use This product is CYLTEZO® (adalimumab-adbm).

The Adalimumab-adbm Pen is a single-dose prefilled pen that delivers a fixed dose of medicine. The Adalimumab-adbm Pen cannot be reused.

Important: Read these instructions before using a Adalimumab-adbm Pen.

- Do not use a Adalimumab-adbm Pen until you have been shown the right way to give the injections and have read and understood this Instructions for Use. If your doctor decides that you or a caregiver may be able to give your injections of Adalimumab-adbm at home, you should receive training on the right way to prepare and inject Adalimumab-adbm. To help you remember when to inject Adalimumab-adbm, you can mark your calendar ahead of time.
- Do not remove the cap until you are ready to inject.

How should I store Adalimumab-adbm?

- Store Adalimumab-adbm in the refrigerator at 36°F to 46°F (2°C to 8°C). Store Adalimumab-adbm in the original carton until use to protect it from light.
- Do not freeze Adalimumab-adbm. Do not use Adalimumab-adbm if frozen, even if it has been thawed.
- Refrigerated Adalimumab-adbm may be used until the expiration date printed on the Adalimumab-adbm carton, dose tray, or pen. Do not use Adalimumab-adbm after the expiration date.
- If needed, for example, when you are traveling, you may also store Adalimumab-adbm at room temperature up to 77°F (25°C) for up to 14 days. Store Adalimumab-adbm in the original carton until use to protect it from light.
- Throw away Adalimumab-adbm if it has been kept at room temperature and not been used within 14 days.
- Record the date you first remove Adalimumab-adbm from the refrigerator in the spaces provided on the carton and dose tray.
- Do not store Adalimumab-adbm in extreme heat or cold.
- Do not use a Adalimumab-adbm Pen if the liquid is milky, discolored, or has flakes or particles in it.
- Do not drop or crush Adalimumab-adbm. The prefilled syringe inside the pen is glass.

Keep Adalimumab-adbm, injection supplies, and all other medicines out of the reach of children.

Step 1

Gather your supplies

Gather your supplies and place them on a clean, flat surface:

- (a) 1 Adalimumab-adbm Pen, removed from the refrigerator.
- (b) FDA-cleared sharps disposal container (not included).
  See "How should I throw away (dispose of) the used pen?"
- (c) Cotton ball or gauze (not included)
- (d) 1 Alcohol wipe

Take your Adalimumab-adbm Pen out of the refrigerator 15 to 30 minutes before injecting to allow the medicine to reach room temperature. Injecting medicine that is cold can cause discomfort.
Make sure you have all of the supplies you need to give yourself an injection. If any parts of the Adalimumab-adbm pen appear to be missing, broken, or damaged, call your pharmacist.

Step 2

Inspect the pen

- Make sure the medicine in the Adalimumab-adbm Pen is clear to slightly cloudy and colorless to slightly yellow.
- It is normal to see 1 or more bubbles in the medicine.
- Do not use the Adalimumab-adbm Pen if:
  - The expiration date on the pen has passed.
  - The medicine is milky, discolored, or has flakes or particles in it.
  - The pen has been frozen.
  - Any part of the pen appears cracked, broken or is leaking.
  - The pen has been dropped.
  - The pen has been exposed to extreme heat or left in direct light.

Step 3

Wash your hands

- Wash your hands with soap and water, and dry them well.

Step 4

Choose the injection site

- Choose an area on your:
  - Upper thighs or
  - Abdomen (belly), except for an area 2 inches around your belly button (navel).
- Choose a different site each time you inject, at least 1 inch away from the previous injection site.
- Do not inject into areas that are tender, bruised, red, hard, or scarred.
- Do not inject through clothes.

Step 5

Clean the injection site

- Use an alcohol wipe to clean the injection site.
- Do not touch this area again before injecting. Allow the skin to dry. Do not fan or blow on the clean area.

Step 6

Remove the cap

- Hold the pen with 1 hand. With the other hand gently remove the cap by pulling it straight off the pen. Do not twist the cap. Twisting the cap could damage the needle.
- Throw away (discard) the cap into an FDA-cleared sharps disposal container. See "How should I throw away (dispose of) the used pen?"
- Do not try to recap the pen.

Step 7

Squeeze the skin

- Gently squeeze the area of cleaned skin around your injection site and hold it firmly. You will inject into this squeezed skin.

Important: Before injecting Adalimumab-adbm, read Step 8 through Step 10 to learn how to use or give (administer) a dose of Adalimumab-adbm the right way.

Step 8

Prepare to administer the dose

- Hold the pen straight at a 90-degree angle to the injection site. Do not cover the window with your hand.
- Press and hold the tip firmly against the squeezed skin at the injection site. The injection button will unlock and be ready for use.

Step 9

Administer the dose

- Administer the entire dose:
  - Press the injection button 1 time. You will hear a 'click' when you press the injection button. The click means the start of the injection.
  - Keep holding the pen against the squeezed skin around the injection site while you slowly count to 10.
  - Do not move the pen during the injection.
- Before removing the pen from your skin, look in the window and make sure the plunger is at the bottom of the pen. This means that the entire dose was delivered. If the plunger does not reach the bottom of the pen, call your doctor.

Step 10

Remove the pen

- Lift the pen straight up from the skin. The needle guard on the tip will automatically move down to cover the needle.
- If there is blood, press a cotton ball or gauze on the injection site.
- Do not rub the injection site.

Step 11

How should I throw away (dispose of) the used pen?

Put the used pen in an FDA-cleared sharps disposal container right away after use. Do not throw away (dispose of) the pen in the household trash.
If you do not have an FDA-cleared sharps disposal container, you may use a household container that is:

- made of a heavy-duty plastic,
- can be closed with a tight fitting, puncture-resistant lid, without sharps being able to come out,
- upright and stable during use,
- leak-resistant, and
- properly labeled to warn of hazardous waste inside the container.

When your sharps disposal container is almost full, you will need to follow your community guidelines for the right way to dispose of your sharps disposal container. There may be state or local laws about how you should throw away used needles and syringes. For more information about safe sharps disposal, and for specific information about sharps disposal in the state that you live in, go to the FDA's website at: http://www.fda.gov/safesharpsdisposal.

- Do not reuse the Adalimumab-adbm Pen.
- Do not throw away (dispose of) your used sharps disposal container in your household trash unless your community guidelines permit this.
- Do not recycle your used sharps disposal container.

Important: Always keep the sharps disposal container out of the reach of children.

If you have any problems with your injection, do not use another Adalimumab-adbm Pen. Call your doctor for help.
For more information call 1-800-542-6257.

This Instructions for Use has been approved by the U.S. Food and Drug Administration.

Manufactured by: Boehringer Ingelheim Pharmaceuticals, Inc., Ridgefield, CT 06877 USA

US License Number 2006

CYLTEZO® is a registered trademark of and is used under license from Boehringer Ingelheim International GmbH.

Other trademarks referenced are owned by third parties not affiliated with Boehringer Ingelheim Pharmaceuticals, Inc.

For more information about Adalimumab-adbm, scan the code or call 1-800-542-6257.

Copyright © 2025 Boehringer Ingelheim International GmbH

ALL RIGHTS RESERVED
COL12914DI302025
Revised: 10/2025

INSTRUCTIONS FOR USE
Adalimumab-adbm (ada-LIM-u-mab adbm)
injection, for subcutaneous use
Single-Dose Adalimumab-adbm Prefilled Syringe
This product is CYLTEZO® (adalimumab-adbm).

Adalimumab-adbm is a single-dose prefilled syringe that delivers a fixed dose of medicine. The prefilled syringe cannot be reused.

Important: Read these instructions before using a Adalimumab-adbm prefilled syringe.

- Do not use a Adalimumab-adbm prefilled syringe until you have been shown the right way to give the injections and have read and understood this Instructions for Use. If your doctor decides that you or a caregiver may be able to give your injections at home, you should receive training on the right way to prepare and give the injection. To help you remember when to inject Adalimumab-adbm, you can mark your calendar ahead of time.
- Do not remove the cap until you are ready to inject.

How should I store Adalimumab-adbm?

- Store Adalimumab-adbm in the refrigerator at 36°F to 46°F (2°C to 8°C). Store Adalimumab-adbm in the original carton until use to protect it from light.
- Do not freeze Adalimumab-adbm. Do not use Adalimumab-adbm if frozen, even if it has been thawed.
- Refrigerated Adalimumab-adbm may be used until the expiration date printed on the Adalimumab-adbm carton, dose tray, or prefilled syringe. Do not use Adalimumab-adbm after the expiration date.
- If needed, for example, when you are traveling, you may also store Adalimumab-adbm at room temperature up to 77°F (25°C) for up to 14 days. Store Adalimumab-adbm in the original carton until use to protect it from light.
- Throw away Adalimumab-adbm if it has been kept at room temperature and not been used within 14 days.
- Record the date you first remove Adalimumab-adbm from the refrigerator in the spaces provided on the carton and dose tray.
- Do not store Adalimumab-adbm in extreme heat or cold.
- Do not use a prefilled syringe if the liquid is milky, discolored, or has flakes or particles in it.
- Do not drop or crush Adalimumab-adbm. The prefilled syringe is glass.

Keep Adalimumab-adbm, injection supplies, and all other medicines out of the reach of children.

Step 1

Gather your supplies

Gather your supplies and place them on a clean, flat surface:

- (a) 1 Adalimumab-adbm prefilled syringe, removed from the refrigerator.
- (b) FDA-cleared sharps disposal container (not included).
  See "How should I throw away (dispose of) the used prefilled syringe?"
- (c) Cotton ball or gauze (not included)
- (d) 1 Alcohol wipe

Take your Adalimumab-adbm prefilled syringe out of the refrigerator 15 to 30 minutes before injecting, to allow the medicine to reach room temperature. Injecting medicine that is cold can cause discomfort.
If you do not have all of the supplies you need to give yourself an injection, call your pharmacist.

Step 2

Inspect the prefilled syringe

- Make sure the medicine in the prefilled syringe is clear to slightly cloudy and colorless to slightly yellow.
- It is normal to see air bubbles. The air bubbles do not need to be removed prior to injection.
- Do not use the prefilled syringe if:
  - The expiration date on the prefilled syringe has passed.
  - The medicine is milky, discolored, or has flakes or particles in it.
  - The prefilled syringe has been frozen.
  - Any part of the prefilled syringe appears cracked, broken or is leaking.
  - The prefilled syringe has been exposed to extreme heat or left in direct light.

Step 3

Wash your hands

- Wash your hands with soap and water, and dry them well.

Step 4

Choose the injection site

- Choose an area on your:
  - Upper thighs or
  - Abdomen (belly), except for an area 2 inches around your belly button (navel).
- Choose a different site each time you inject at least 1 inch away from the previous injection site.
- Do not inject into areas that are tender, bruised, red, hard, or scarred.
- Do not inject through clothes.

Step 5

Clean the injection site

- Use an alcohol wipe to clean the injection site.
- Do not touch this area again before injecting. Allow the skin to dry. Do not fan or blow on the clean area.

Step 6

Remove the cap

- Hold the prefilled syringe with 1 hand. With the other hand gently remove the cap by pulling it straight off. Do not touch the needle or let the needle touch anything.
- Throw away (discard) the cap into an FDA-cleared sharps disposal container. See "How should I throw away (dispose of) the used prefilled syringe?"
- Do not try to recap the needle.

Step 7

Squeeze the skin

- Gently squeeze the area of cleaned skin around your injection site and hold it firmly. You will inject into this squeezed skin.

Step 8

Insert the needle

- Hold the body of the prefilled syringe in 1 hand between the thumb and index finger. Hold the syringe in your hand like a pencil.
- Using a quick, smooth motion, insert the needle into the squeezed skin at about a 45-degree angle.

Step 9

Inject the medicine

- Using your thumb, slowly push the plunger rod all the way down until plunger reaches the bottom.

Step 10

Remove the needle from the skin

- Remove the needle from your skin at the same angle as it was inserted.
- Do not touch the needle.
- If there is blood, press a cotton ball or gauze on your injection site.
- Do not rub the injection site.

Step 11

How should I throw away (dispose of) the used prefilled syringe?

Put the used prefilled syringe in an FDA-cleared sharps disposal container right away after use. Do not throw away (dispose of) the prefilled syringe in the household trash.
If you do not have an FDA-cleared sharps disposal container, you may use a household container that is:

- made of a heavy-duty plastic,
- can be closed with a tight fitting, puncture-resistant lid, without sharps being able to come out,
- upright and stable during use,
- leak-resistant, and
- properly labeled to warn of hazardous waste inside the container.

When your sharps disposal container is almost full, you will need to follow your community guidelines for the right way to dispose of your sharps disposal container. There may be state or local laws about how you should throw away used needles and syringes. For more information about safe sharps disposal, and for specific information about sharps disposal in the state that you live in, go to the FDA's website at: http://www.fda.gov/safesharpsdisposal.

- Do not reuse the prefilled syringe.
- Do not throw away (dispose of) your used sharps disposal container in your household trash unless your community guidelines permit this.
- Do not recycle your used sharps disposal container.

Important: Always keep the sharps disposal container out of the reach of children.

If you have any problems with your injection, do not use another Adalimumab-adbm prefilled syringe. Call your doctor for help.
For more information call 1-800-542-6257.

This Instructions for Use has been approved by the U.S. Food and Drug Administration.

Manufactured by: Boehringer Ingelheim Pharmaceuticals, Inc., Ridgefield, CT 06877 USA

US License Number 2006

CYLTEZO® is a registered trademark of and is used under license from Boehringer Ingelheim International GmbH.

Other trademarks referenced are owned by third parties not affiliated with Boehringer Ingelheim Pharmaceuticals, Inc.

For more information about Adalimumab-adbm, scan the code or call 1-800-542-6257.

Copyright © 2025 Boehringer Ingelheim International GmbH

ALL RIGHTS RESERVED
COL12316DI302025
Revised: 10/2025

PRINCIPAL DISPLAY PANEL - 40 mg/0.8 mL Kit Carton

NDC 0597-0595-20

ATTENTION PHARMACIST:
Each Patient is Required to Receive the
Enclosed Medication Guide.

The Entire Carton is to be Dispensed as a Unit.

Needle Cap for Syringe Contains Dry Natural Rubber.

Adalimumab-adbm
Injection

40 mg/0.8 mL

For Subcutaneous Use Only

Rx only

This product is Cyltezo*

2 Single-Dose Prefilled Syringes

Boehringer
Ingelheim

PRINCIPAL DISPLAY PANEL - 20 mg/0.4 mL Kit Carton

NDC 0597-0555-80

ATTENTION PHARMACIST:
Each Patient is Required to Receive the
Enclosed Medication Guide.

The Entire Carton is to be Dispensed as a Unit.

Needle Cap for Syringe Contains Dry Natural Rubber.

Adalimumab-adbm
Injection

20 mg/0.4 mL

For Subcutaneous Use Only

Rx only

This product is Cyltezo*

2 Single-Dose Prefilled Syringes

Boehringer
Ingelheim

PRINCIPAL DISPLAY PANEL - 10 mg/0.2 mL Kit Carton

NDC 0597-0585-89

ATTENTION PHARMACIST:
Each Patient is Required to Receive the
Enclosed Medication Guide.

The Entire Carton is to be Dispensed as a Unit.

Needle Cap for Syringe Contains Dry Natural Rubber.

Adalimumab-adbm
Injection

10 mg/0.2 mL

For Subcutaneous Use Only

Rx only

This product is Cyltezo*

2 Single-Dose Prefilled Syringes

Boehringer
Ingelheim

PRINCIPAL DISPLAY PANEL - 40 mg/0.8 mL Kit Carton

NDC 0597-0545-22

ATTENTION PHARMACIST:
Each Patient is Required to Receive the
Enclosed Medication Guide.

The Entire Carton is to be Dispensed as
a Unit.

Needle Cap for Pen Contains Dry
Natural Rubber.

Adalimumab-adbm PEN
Injection

40 mg/0.8 mL

For Subcutaneous Use Only

Rx only

This product is Cyltezo*

2 Single-Dose Prefilled Pens

Boehringer
Ingelheim

PRINCIPAL DISPLAY PANEL - 40 mg/0.4 mL Kit Carton - NDC 0597-0575-50

NDC 0597-0575-50

ATTENTION PHARMACIST:
Each Patient is Required to Receive the
Enclosed Medication Guide.

The Entire Carton is to be Dispensed as
a Unit.

Needle Cap for Pen Contains Dry
Natural Rubber.

Adalimumab-adbm PEN
Injection

40 mg/0.4 mL

For Subcutaneous Use Only

Rx only

This product is Cyltezo*

2 Single-Dose Prefilled Pens

Boehringer
Ingelheim

PRINCIPAL DISPLAY PANEL - 40 mg/0.4 mL Kit Carton - NDC 0597-0565-20

NDC 0597-0565-20

ATTENTION PHARMACIST:
Each Patient is Required to Receive the
Enclosed Medication Guide.

The Entire Carton is to be Dispensed as a Unit.

Needle Cap for Syringe Contains Dry Natural Rubber.

Adalimumab-adbm
Injection

40 mg/0.4 mL

For Subcutaneous Use Only

Rx only

This product is Cyltezo*

2 Single-Dose Prefilled Syringes

Boehringer
Ingelheim